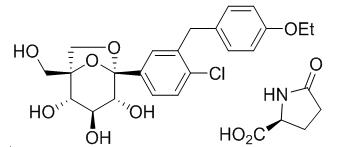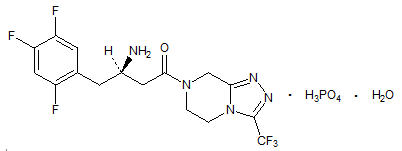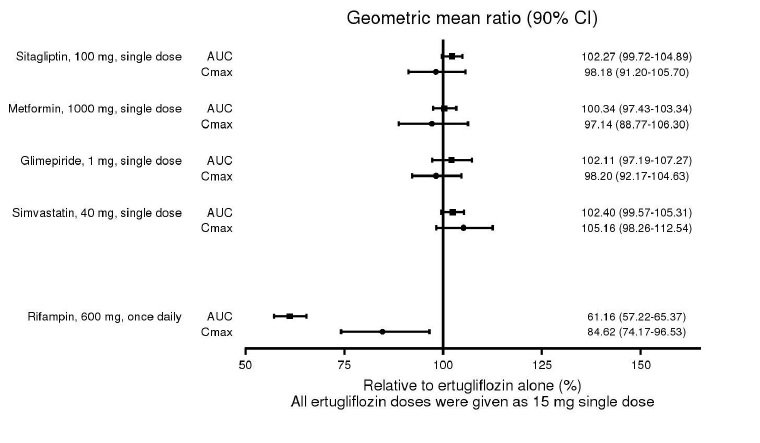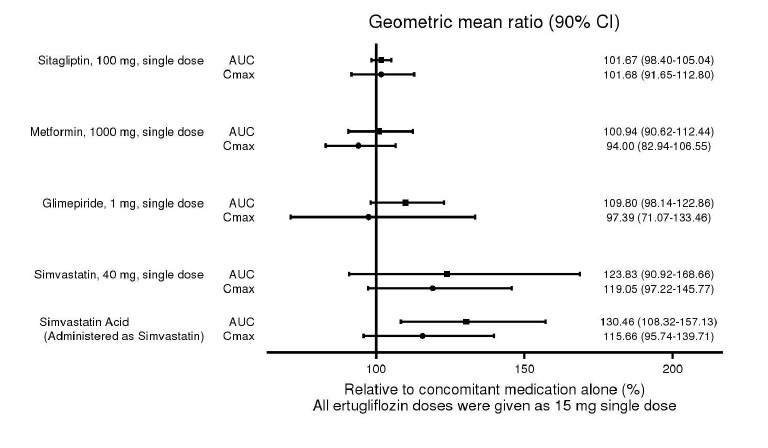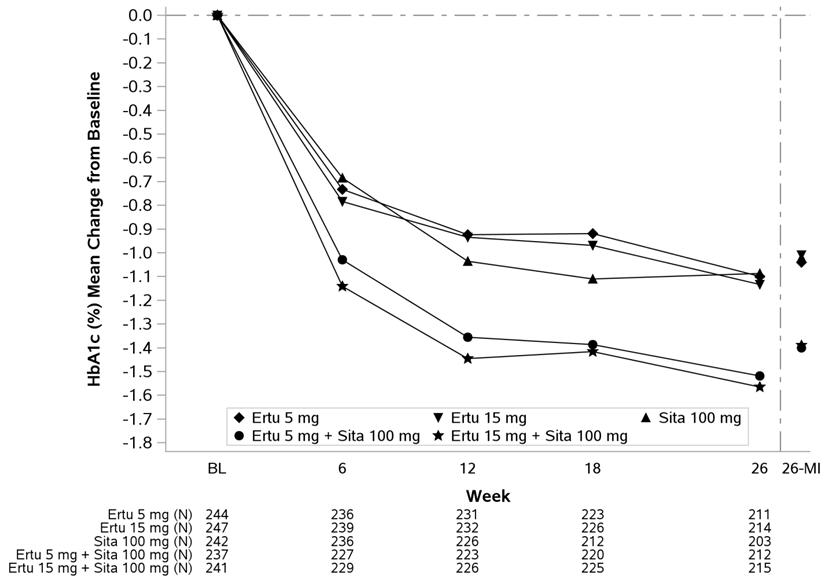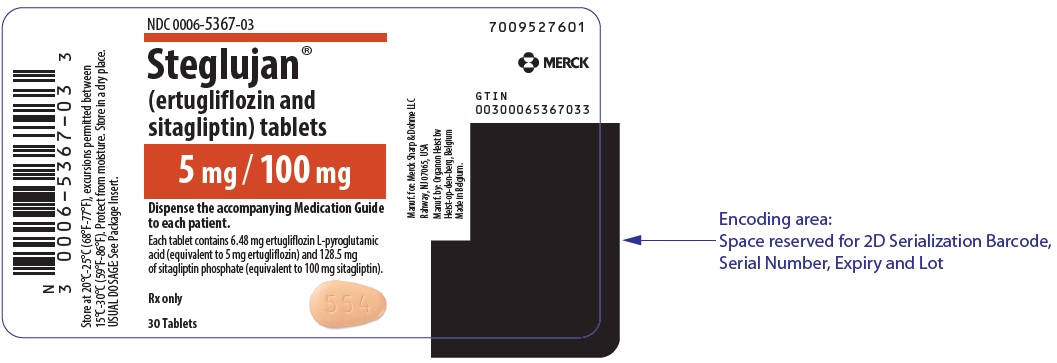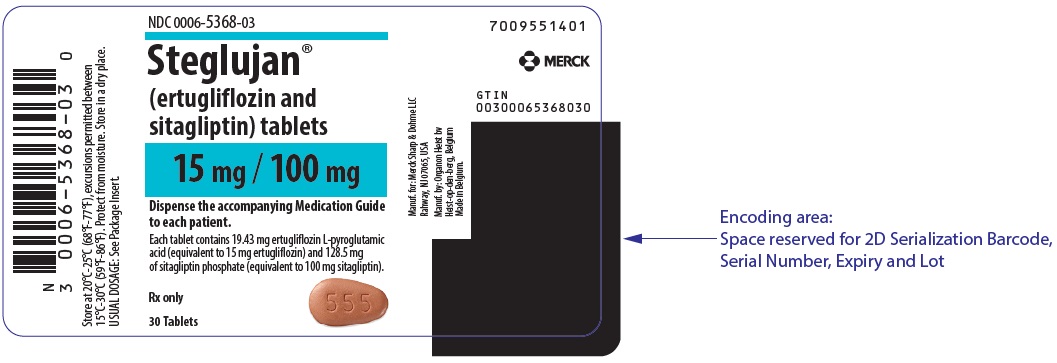 DRUG LABEL: STEGLUJAN
NDC: 0006-5367 | Form: TABLET, FILM COATED
Manufacturer: Merck Sharp & Dohme LLC
Category: prescription | Type: HUMAN PRESCRIPTION DRUG LABEL
Date: 20241220

ACTIVE INGREDIENTS: ERTUGLIFLOZIN PIDOLATE 5 mg/1 1; SITAGLIPTIN PHOSPHATE 100 mg/1 1
INACTIVE INGREDIENTS: MICROCRYSTALLINE CELLULOSE; ANHYDROUS DIBASIC CALCIUM PHOSPHATE; CROSCARMELLOSE SODIUM; SODIUM STEARYL FUMARATE; MAGNESIUM STEARATE; HYPROMELLOSE, UNSPECIFIED; HYDROXYPROPYL CELLULOSE, UNSPECIFIED; TITANIUM DIOXIDE; FERRIC OXIDE RED; FERROSOFERRIC OXIDE; CARNAUBA WAX; PROPYL GALLATE; FERRIC OXIDE YELLOW

HIGHLIGHTS OF PRESCRIBING INFORMATION

These highlights do not include all the information needed to use STEGLUJAN safely and effectively. See full prescribing information for STEGLUJAN.
STEGLUJAN® (ertugliflozin and sitagliptin) tablets, for oral use
Initial U.S. Approval: 2017

RECENT MAJOR CHANGES

Dosage and Administration (2.3) | 12/2024
Warnings and Precautions (5.3, 5.8) | 12/2024

1 INDICATIONS AND USAGE

STEGLUJAN is a combination of ertugliflozin, a sodium glucose co-transporter 2 (SGLT2) inhibitor, and sitagliptin, a dipeptidyl peptidase-4 (DPP-4) inhibitor, is indicated as an adjunct to diet and exercise to improve glycemic control in adults with type 2 diabetes mellitus.

Limitations of Use:

- Not recommended for use to improve glycemic control in patients with type 1 diabetes mellitus. (1)
- Has not been studied in patients with a history of pancreatitis. (1, 5.2)

2 DOSAGE AND ADMINISTRATION

- Assess renal function before initiating and as clinically indicated. (2.1)
- Correct volume depletion before initiating. (2.1)
- Recommended starting dosage is 5 mg ertugliflozin/100 mg sitagliptin orally once daily, taken in the morning, with or without food. (2.2)
- Increase dosage to 15 mg ertugliflozin/100 mg sitagliptin orally once daily in those tolerating STEGLUJAN and needing additional glycemic control. (2.2)
- Use is not recommended in patients with an estimated glomerular filtration rate (eGFR) less than 45 mL/min/1.73 m^2. (2.2)
- Withhold STEGLUJAN for at least 4 days, if possible, prior to surgery or procedures associated with prolonged fasting. (2.3)

3 DOSAGE FORMS AND STRENGTHS

Tablets:

- Ertugliflozin 5 mg and sitagliptin 100 mg (3)
- Ertugliflozin 15 mg and sitagliptin 100 mg (3)

4 CONTRAINDICATIONS

- Severe renal impairment (eGFR less than 30 mL/min/1.73 m^2), end-stage renal disease, or dialysis. (4)
- Hypersensitivity to sitagliptin, ertugliflozin, or any excipient in STEGLUJAN. (4, 5.11, 6.2)

5 WARNINGS AND PRECAUTIONS

- Diabetic Ketoacidosis in Patients with Type 1 Diabetes Mellitus and Other Ketoacidosis: Consider ketone monitoring in patients at risk for ketoacidosis, as indicated. Assess for ketoacidosis regardless of presenting blood glucose levels and discontinue STEGLUJAN if ketoacidosis is suspected. Monitor patients for resolution of ketoacidosis before restarting. (5.1)
- Pancreatitis: There have been postmarketing reports of acute pancreatitis in patients taking sitagliptin, including fatal and non-fatal hemorrhagic or necrotizing pancreatitis. If pancreatitis is suspected, promptly discontinue. (5.2)
- Lower Limb Amputation: Monitor patients for infections or ulcers of lower limbs, and discontinue if these occur. (5.3)
- Acute Renal Failure: There have been postmarketing reports of acute renal failure in patients taking sitagliptin, sometimes requiring dialysis. Monitor renal function. (5.4)
- Volume Depletion: May result in acute kidney injury. Before initiating, assess and correct volume status in patients with renal impairment, or low systolic blood pressure elderly patients, or patients on diuretics. Monitor for signs and symptoms during therapy. (5.5)
- Urosepsis and Pyelonephritis: Evaluate patients for signs and symptoms of urinary tract infections and treat promptly, if indicated. (5.6)
- Heart Failure: Heart failure has been observed with two other members of the DPP-4 inhibitor class. Consider risks and benefits in patients who have known risk factors for heart failure. Monitor patients for signs and symptoms. (5.7)
- Hypoglycemia: Consider a lower dose of insulin or insulin secretagogue to reduce risk of hypoglycemia when used in combination. (5.8)
- Necrotizing Fasciitis of the Perineum (Fournier’s Gangrene): Serious, life-threatening cases have occurred in both females and males. Assess patients presenting with pain or tenderness, erythema, or swelling in the genital or perineal area, along with fever or malaise. If suspected, institute prompt treatment. (5.9)
- Genital Mycotic Infections: Monitor and treat if indicated. (5.10)
- Hypersensitivity: There have been postmarketing reports of serious allergic and hypersensitivity reactions in patients treated with sitagliptin such as anaphylaxis, angioedema, and exfoliative skin conditions including Stevens-Johnson syndrome. In such cases, promptly discontinue, assess for other potential causes, institute appropriate monitoring and treatment, and initiate alternative treatment for diabetes. (5.11)
- Severe and Disabling Arthralgia: Severe and disabling arthralgia has been reported in patients taking DPP-4 inhibitors. Consider as a possible cause for severe joint pain and discontinue if appropriate. (5.12)
- Pemphigoid: There have been postmarketing reports of bullous pemphigoid requiring hospitalization in patients taking DPP-4 inhibitors. Tell patients to report development of blisters or erosions. If bullous pemphigoid is suspected, discontinue. (5.13)

6 ADVERSE REACTIONS

- Most common adverse reactions associated with ertugliflozin (incidence ≥5%): female genital mycotic infections. (6.1)
- Most common adverse reactions associated with sitagliptin (incidence ≥5%): upper respiratory tract infection, nasopharyngitis and headache. In the add-on to sulfonylurea and add-on to insulin studies, hypoglycemia was also more commonly reported in patients treated with sitagliptin compared to placebo. (6.1)

To report SUSPECTED ADVERSE REACTIONS, contact Merck Sharp & Dohme LLC at 1-877-888-4231 or FDA at 1-800-FDA-1088 or www.fda.gov/medwatch .

7 DRUG INTERACTIONS

See full prescribing information for information on drug interactions and interference of STEGLUJAN with laboratory tests. (7)

8 USE IN SPECIFIC POPULATIONS

- Pregnancy: Advise females of the potential risk to a fetus especially during the second and third trimesters. (8.1)
- Lactation: Breastfeeding not recommended. (8.2)
- Geriatrics: Higher incidence of adverse reactions related to reduced intravascular volume. (8.5)
- Renal Impairment: Higher incidence of adverse reactions related to reduced intravascular volume and renal function. (8.6)

FULL PRESCRIBING INFORMATION

1 INDICATIONS AND USAGE

STEGLUJAN® is indicated as an adjunct to diet and exercise to improve glycemic control in adults with type 2 diabetes mellitus.

Limitations of Use

- Not recommended for use to improve glycemic control in patients with type 1 diabetes mellitus [see Warnings and Precautions (5.1)].
- Has not been studied in patients with a history of pancreatitis. It is unknown whether patients with a history of pancreatitis are at increased risk for the development of pancreatitis while using STEGLUJAN [see Warnings and Precautions (5.2)].

2 DOSAGE AND ADMINISTRATION

2.1 Prior to Initiation of STEGLUJAN

- Assess renal function before initiating STEGLUJAN and as clinically indicated [see Warnings and Precautions (5.4)].
- Assess volume status. In patients with volume depletion, correct this condition before initiating STEGLUJAN [see Warnings and Precautions (5.5) and Use in Specific Populations (8.5, 8.6)].

2.2 Recommended Dosage

- The recommended starting dosage of STEGLUJAN is 5 mg ertugliflozin/100 mg sitagliptin orally once daily, taken in the morning, with or without food.
- For patients treated with ertugliflozin who are being switched to STEGLUJAN, the dosage of ertugliflozin can be maintained.
- For additional glycemic control, the dosage may be increased to 15 mg ertugliflozin/100 mg sitagliptin orally once daily in patients tolerating STEGLUJAN.
- Use is not recommended in patients with an estimated glomerular filtration rate (eGFR) less than 45 mL/min/1.73 m^2.
- Use of STEGLUJAN is contraindicated in patients with severe renal impairment (eGFR less than 30 mL/min/1.73 m^2), end-stage renal disease (ESRD) or on dialysis [see Contraindications (4)].

2.3 Temporary Interruption for Surgery

Withhold STEGLUJAN for at least 4 days, if possible, prior to surgery or procedures associated with prolonged fasting. Resume STEGLUJAN when the patient is clinically stable and has resumed oral intake [see Warnings and Precautions (5.1) and Clinical Pharmacology (12.2)].

3 DOSAGE FORMS AND STRENGTHS

- STEGLUJAN 5 mg/100 mg tablets: contain ertugliflozin 5 mg and sitagliptin 100 mg and are beige, almond-shaped debossed with "554" on one side and plain on the other side.
- STEGLUJAN 15 mg/100 mg tablets: contain ertugliflozin 15 mg and sitagliptin 100 mg and are brown, almond-shaped debossed with "555" on one side and plain on the other side.

4 CONTRAINDICATIONS

STEGLUJAN is contraindicated in patients with:

- Severe renal impairment (eGFR less than 30 mL/min/1.73 m^2), end-stage renal disease (ESRD), or on dialysis [see Warnings and Precautions (5.4) and Use in Specific Populations (8.6)].
- Hypersensitivity to sitagliptin, ertugliflozin, or any excipient, in STEGLUJAN. Reactions such as anaphylaxis or angioedema have occurred [see Warnings and Precautions (5.11) and Adverse Reactions (6.2)].

5 WARNINGS AND PRECAUTIONS

5.1 Diabetic Ketoacidosis in Patients with Type 1 Diabetes Mellitus and Other Ketoacidosis

In patients with type 1 diabetes mellitus, STEGLUJAN significantly increases the risk of diabetic ketoacidosis, a life-threatening event, beyond the background rate. In placebo-controlled trials of patients with type 1 diabetes mellitus, the risk of ketoacidosis was markedly increased in patients who received sodium glucose transporter 2 (SGLT2) inhibitors compared to patients who received placebo; this risk may be greater with higher doses. STEGLUJAN is not indicated for glycemic control in patients with type 1 diabetes mellitus.

Type 2 diabetes mellitus and pancreatic disorders (e.g., history of pancreatitis or pancreatic surgery) are also risk factors for ketoacidosis. There have been postmarketing reports of fatal events of ketoacidosis in patients with type 2 diabetes mellitus using SGLT2 inhibitors.

Precipitating conditions for diabetic ketoacidosis or other ketoacidosis include under-insulinization due to insulin dose reduction or missed insulin doses, acute febrile illness, reduced caloric intake, ketogenic diet, surgery, volume depletion, and alcohol abuse.

Signs and symptoms are consistent with dehydration and severe metabolic acidosis and include nausea, vomiting, abdominal pain, generalized malaise, and shortness of breath. Blood glucose levels at presentation may be below those typically expected for diabetic ketoacidosis (e.g., less than 250 mg/dL). Ketoacidosis and glucosuria may persist longer than typically expected. Urinary glucose excretion persists for 4 days after discontinuing STEGLUJAN [see Clinical Pharmacology (12.2)]; however, there have been postmarketing reports of ketoacidosis and/or glucosuria lasting greater than 6 days and some up to 2 weeks after discontinuation of SGLT2 inhibitors.

Consider ketone monitoring in patients at risk for ketoacidosis if indicated by the clinical situation. Assess for ketoacidosis regardless of presenting blood glucose levels in patients who present with signs and symptoms consistent with severe metabolic acidosis. If ketoacidosis is suspected, discontinue STEGLUJAN, promptly evaluate, and treat ketoacidosis, if confirmed. Monitor patients for resolution of ketoacidosis before restarting STEGLUJAN.

Withhold STEGLUJAN, if possible, in temporary clinical situations that could predispose patients to ketoacidosis. Resume STEGLUJAN when the patient is clinically stable and has resumed oral intake [see Dosage and Administration (2.3)].

Educate all patients on the signs and symptoms of ketoacidosis and instruct patients to discontinue STEGLUJAN and seek medical attention immediately if signs and symptoms occur.

5.2 Pancreatitis

There have been postmarketing reports of acute pancreatitis, including fatal and non-fatal hemorrhagic or necrotizing pancreatitis, in patients taking sitagliptin, a component of STEGLUJAN. After initiation of STEGLUJAN, patients should be observed carefully for signs and symptoms of pancreatitis. If pancreatitis is suspected, STEGLUJAN should promptly be discontinued and appropriate management should be initiated. It is unknown whether patients with a history of pancreatitis are at increased risk for the development of pancreatitis while using STEGLUJAN.

5.3 Lower Limb Amputation

In a long-term cardiovascular outcomes study [see Clinical Studies (14.2)], in patients with type 2 diabetes mellitus and established cardiovascular disease, the occurrence of non-traumatic lower limb amputations was reported with event rates of 4.7, 5.7, and 6.0 events per 1000 patient-years in the placebo, ertugliflozin 5 mg, and ertugliflozin 15 mg treatment arms, respectively.

Amputation of the toe and foot were most frequent (81 out of 109 patients with lower limb amputations). Some patients had multiple amputations, some involving both lower limbs.

Lower limb infections, gangrene, and diabetic foot ulcers were the most common precipitating medical events leading to the need for an amputation. Patients with amputations were more likely to be male, have higher A1C (%) at baseline, have a history of peripheral arterial disease, amputation or peripheral revascularization procedure, diabetic foot, and to have been taking diuretics or insulin.

Across seven ertugliflozin clinical trials, non-traumatic lower limb amputations were reported in 1 (0.1%) patient in the comparator group, 3 (0.2%) patients in the ertugliflozin 5 mg group, and 8 (0.5%) patients in the ertugliflozin 15 mg group.

Counsel patients about the importance of routine preventative foot care. Monitor patients receiving STEGLUJAN for signs and symptoms of infection (including osteomyelitis), new pain or tenderness, sores or ulcers involving the lower limbs, and discontinue STEGLUJAN if these complications occur.

5.4 Acute Renal Failure

There have been postmarketing reports with sitagliptin of worsening renal function, including acute renal failure, sometimes requiring dialysis. A subset of these reports involved patients with renal insufficiency, some of whom were prescribed inappropriate doses of sitagliptin. A return to baseline levels of renal insufficiency has been observed with supportive treatment and discontinuation of potentially causative agents. Consideration can be given to cautiously reinitiating STEGLUJAN if another etiology is deemed likely to have precipitated the acute worsening of renal function.

Sitagliptin has not been found to be nephrotoxic in preclinical studies at clinically relevant doses, or in clinical trials.

5.5 Volume Depletion

STEGLUJAN can cause intravascular volume contraction which may sometimes manifest as symptomatic hypotension or acute transient changes in creatinine [see Adverse Reactions (6.1)]. There have been postmarketing reports of acute kidney injury, some requiring hospitalization and dialysis, in patients with type 2 diabetes mellitus receiving SGLT2 inhibitors, including STEGLUJAN. Patients with impaired renal function (eGFR less than 60 mL/min/1.73 m^2) [see Use in Specific Populations (8.6)], elderly patients, patients with low systolic blood pressure, or patients on loop diuretics may be at increased risk for volume depletion or hypotension. Before initiating STEGLUJAN in patients with one or more of these characteristics, assess volume status and renal function. In patients with volume depletion, correct this condition before initiating STEGLUJAN. Monitor for signs and symptoms of volume depletion, and renal function after initiating therapy.

5.6 Urosepsis and Pyelonephritis

There have been postmarketing reports of serious urinary tract infections, including urosepsis and pyelonephritis, requiring hospitalization in patients receiving medicines containing SGLT2 inhibitors. Treatment with medicines containing SGLT2 inhibitors increases the risk for urinary tract infections. Evaluate patients for signs and symptoms of urinary tract infections and treat promptly, if indicated [see Adverse Reactions (6)].

5.7 Heart Failure

An association between dipeptidyl peptidase-4 (DPP-4) inhibitor treatment and heart failure has been observed in cardiovascular outcomes trials for two other members of the DPP-4 inhibitor class. These trials evaluated patients with type 2 diabetes mellitus and atherosclerotic cardiovascular disease. Consider the risks and benefits of STEGLUJAN prior to initiating treatment in patients at risk for heart failure, such as those with a prior history of heart failure and a history of renal impairment, and observe these patients for signs and symptoms of heart failure during therapy. Advise patients of the characteristic symptoms of heart failure and to immediately report such symptoms. If heart failure develops, evaluate and manage according to current standards of care and consider discontinuation of STEGLUJAN.

5.8 Hypoglycemia with Concomitant Use with Insulin or Insulin Secretagogues

Insulin and insulin secretagogues (e.g., sulfonylurea) are known to cause hypoglycemia. Ertugliflozin, may increase the risk of hypoglycemia when used in combination with insulin or an insulin secretagogue [see Adverse Reactions (6.1)]. The risk of hypoglycemia may be lowered by a reduction in the dose of insulin or sulfonylurea (or other concomitantly administered insulin secretagogues). Inform patients using these medications concomitantly of this risk and educate them on the signs and symptoms of hypoglycemia.

5.9 Necrotizing Fasciitis of the Perineum (Fournier's Gangrene)

Reports of necrotizing fasciitis of the perineum (Fournier's Gangrene), a rare but serious and life-threatening necrotizing infection requiring urgent surgical intervention, have been identified in postmarketing surveillance in patients with diabetes mellitus receiving SGLT2 inhibitors, including ertugliflozin. Cases have been reported in females and males. Serious outcomes have included hospitalization, multiple surgeries, and death.

Patients treated with STEGLUJAN presenting with pain or tenderness, erythema, or swelling in the genital or perineal area, along with fever or malaise, should be assessed for necrotizing fasciitis. If suspected, start treatment immediately with broad-spectrum antibiotics and, if necessary, surgical debridement. Discontinue STEGLUJAN, closely monitor blood glucose levels, and provide appropriate alternative therapy for glycemic control.

5.10 Genital Mycotic Infections

Ertugliflozin, increases the risk of genital mycotic infections. Patients who have a history of genital mycotic infections or who are uncircumcised are more likely to develop genital mycotic infections [see Adverse Reactions (6.1)]. Monitor and treat appropriately.

5.11 Hypersensitivity Reactions

There have been postmarketing reports of serious hypersensitivity reactions in patients treated with sitagliptin. These reactions include anaphylaxis, angioedema, and exfoliative skin conditions including Stevens-Johnson syndrome. Onset of these reactions occurred within the first 3 months after initiation of treatment with sitagliptin, with some reports occurring after the first dose. If a hypersensitivity reaction is suspected, discontinue STEGLUJAN, assess for other potential causes for the event, and institute alternative treatment for diabetes [see Adverse Reactions (6.2)].

Angioedema has also been reported with other dipeptidyl peptidase-4 (DPP-4) inhibitors. Use caution in a patient with a history of angioedema with another DPP-4 inhibitor because it is unknown whether such patients will be predisposed to angioedema with STEGLUJAN.

5.12 Severe and Disabling Arthralgia

There have been postmarketing reports of severe and disabling arthralgia in patients taking DPP-4 inhibitors. The time to onset of symptoms following initiation of drug therapy varied from one day to years. Patients experienced relief of symptoms upon discontinuation of the medication. A subset of patients experienced a recurrence of symptoms when restarting the same drug or a different DPP-4 inhibitor. Consider DPP-4 inhibitors as a possible cause for severe joint pain and discontinue drug if appropriate.

5.13 Bullous Pemphigoid

Postmarketing cases of bullous pemphigoid requiring hospitalization have been reported with DPP-4 inhibitor use. In reported cases, patients typically recovered with topical or systemic immunosuppressive treatment and discontinuation of the DPP-4 inhibitor. Tell patients to report development of blisters or erosions while receiving STEGLUJAN. If bullous pemphigoid is suspected, STEGLUJAN should be discontinued and referral to a dermatologist should be considered for diagnosis and appropriate treatment.

6 ADVERSE REACTIONS

The following important adverse reactions are described elsewhere in the labeling:

- Diabetic Ketoacidosis in Patients with Type 1 Diabetes and Other Ketoacidosis [see Warnings and Precautions (5.1)]
- Pancreatitis [see Warnings and Precautions (5.2)]
- Lower Limb Amputation [see Warnings and Precautions (5.3)]
- Acute Renal Failure [see Warnings and Precautions (5.4)]
- Volume Depletion [see Warnings and Precautions (5.5)]
- Urosepsis and Pyelonephritis [see Warnings and Precautions (5.6)]
- Heart Failure [see Warnings and Precautions (5.7)]
- Hypoglycemia with Concomitant Use with Insulin or Insulin Secretagogues [see Warnings and Precautions (5.8)]
- Necrotizing Fasciitis of the Perineum (Fournier's Gangrene) [see Warnings and Precautions (5.9)]
- Genital Mycotic Infections [see Warnings and Precautions (5.10)]
- Hypersensitivity Reactions [see Warnings and Precautions (5.11)]
- Severe and Disabling Arthralgia [see Warnings and Precautions (5.12)]
- Bullous Pemphigoid [see Warnings and Precautions (5.13)]

6.1 Clinical Trials Experience

Because clinical trials are conducted under widely varying conditions, adverse reaction rates observed in the clinical trials of a drug cannot be directly compared to rates in the clinical trials of another drug and may not reflect the rates observed in practice.

Ertugliflozin and Sitagliptin

The safety of concomitantly administered ertugliflozin and sitagliptin has been evaluated in 990 patients with type 2 diabetes mellitus treated for 26 weeks in three studies; a factorial study of ertugliflozin 5 mg or 15 mg in combination with sitagliptin 100 mg once daily compared to the individual components, a placebo-controlled study of ertugliflozin 5 mg or 15 mg as add-on therapy to sitagliptin 100 mg and metformin HCl once daily, and a placebo-controlled study of initial therapy with ertugliflozin 5 mg or 15 mg once daily in combination with sitagliptin 100 mg once daily [see Clinical Studies (14)]. The incidence and type of adverse reactions in these three studies were similar to the adverse reactions seen with ertugliflozin and described below in Table 1.

Ertugliflozin

Pool of Placebo-Controlled Trials

The data in Table 1 are derived from a pool of three 26-week, placebo-controlled trials. Ertugliflozin was used as monotherapy in one trial and as add-on therapy in two trials [see Clinical Studies (14)]. These data reflect exposure of 1,029 patients to ertugliflozin with a mean exposure duration of approximately 25 weeks. Patients received ertugliflozin 5 mg (N=519), ertugliflozin 15 mg (N=510), or placebo (N=515) once daily. The mean age of the population was 57 years and 2% were older than 75 years of age. Fifty-three percent (53%) of the population was male and 73% were White, 15% were Asian, and 7% were Black or African American. At baseline the population had diabetes for an average of 7.5 years, had a mean HbA1c of 8.1%, and 19.4% had established microvascular complications of diabetes. Baseline renal function (mean eGFR 88.9 mL/min/1.73 m^2) was normal or mildly impaired in 97% of patients and moderately impaired in 3% of patients.

Table 1 shows common adverse reactions associated with the use of ertugliflozin. These adverse reactions were not present at baseline, occurred more commonly on ertugliflozin than on placebo, and occurred in at least 2% of patients treated with either ertugliflozin 5 mg or ertugliflozin 15 mg.

Table 1: Adverse Reactions Reported in ≥2% of Patients with Type 2 Diabetes Mellitus Treated with Ertugliflozin [The three placebo controlled studies included one monotherapy trial and two add-on combination trials with metformin HCl or with metformin HCl and sitagliptin.] and Greater than Placebo in Pooled Placebo-Controlled Clinical Studies of Ertugliflozin Monotherapy or Combination Therapy
 | Number (%) of Patients
 | Placebo N = 515 | Ertugliflozin 5 mg N = 519 | Ertugliflozin 15 mg N = 510
Female genital mycotic infections [Includes: genital candidiasis, genital infection fungal, vaginal infection, vulvitis, vulvovaginal candidiasis, vulvovaginal mycotic infection, and vulvovaginitis. Percentages calculated with the number of female patients in each group as denominator: placebo (N=235), ertugliflozin 5 mg (N=252), ertugliflozin 15 mg (N=245).] | 3.0% | 9.1% | 12.2%
Male genital mycotic infections [Includes: balanitis candida, balanoposthitis, genital infection, and genital infection fungal. Percentages calculated with the number of male patients in each group as denominator: placebo (N=280), ertugliflozin 5 mg (N=267), ertugliflozin 15 mg (N=265).] | 0.4% | 3.7% | 4.2%
Urinary tract infections [Includes: cystitis, dysuria, streptococcal urinary tract infection, urethritis, urinary tract infection.] | 3.9% | 4.0% | 4.1%
Headache | 2.3% | 3.5% | 2.9%
Vaginal pruritus [Includes: vulvovaginal pruritus and pruritus genital. Percentages calculated with the number of female patients in each group as denominator: placebo (N=235), ertugliflozin 5 mg (N=252), ertugliflozin 15 mg (N=245).] | 0.4% | 2.8% | 2.4%
Increased urination [Includes: pollakiuria, micturition urgency, polyuria, urine output increased, and nocturia.] | 1.0% | 2.7% | 2.4%
Nasopharyngitis | 2.3% | 2.5% | 2.0%
Back pain | 2.3% | 1.7% | 2.5%
Weight decreased | 1.0% | 1.2% | 2.4%
Thirst [Includes: thirst, dry mouth, polydipsia, and dry throat.] | 0.6% | 2.7% | 1.4%

Volume Depletion

Ertugliflozin causes an osmotic diuresis, which may lead to intravascular volume contraction and adverse reactions related to volume depletion, particularly in patients with impaired renal function (eGFR less than 60 mL/min/1.73 m^2). In patients with moderate renal impairment, adverse reactions related to volume depletion (e.g., dehydration, dizziness postural, presyncope, syncope, hypotension, and orthostatic hypotension) were reported in 0%, 4.4%, and 1.9% of patients treated with placebo, ertugliflozin 5 mg, and ertugliflozin 15 mg, respectively. Ertugliflozin may also increase the risk of hypotension in other patients at risk for volume contraction [see Use in Specific Populations (8.5, 8.6)].

Hypoglycemia

The incidence of hypoglycemia by study is shown in Table 2.

Table 2: Incidence of Overall [Overall hypoglycemic events: plasma or capillary glucose of less than or equal to 70 mg/dL.] and Severe [Severe hypoglycemic events: required assistance, lost consciousness, or experienced a seizure regardless of blood glucose.] Hypoglycemia in Placebo-Controlled Clinical Studies in Patients with Type 2 Diabetes Mellitus
Factorial Study with Sitagliptin as Add-on Combination Therapy with Metformin HCl (26 weeks) |  | Ertugliflozin 5 mg + Sitagliptin (N = 243) | Ertugliflozin 15 mg + Sitagliptin (N = 244)
Overall [N (%)] |  | 13 (5.3) | 22 (9.0)
Severe [N (%)] |  | 0 (0.0) | 1 (0.4)
Add-on Combination Therapy with Metformin HCl and Sitagliptin (26 weeks) | Placebo (N = 153) | Ertugliflozin 5 mg (N = 156) | Ertugliflozin 15 mg (N = 153)
Overall [N (%)] | 5 (3.3) | 7 (4.5) | 3 (2.0)
Severe [N (%)] | 1 (0.7) | 1 (0.6) | 0 (0.0)
Initial Combination Therapy with Sitagliptin (26 weeks) | Placebo (N = 97) | Ertugliflozin 5 mg + Sitagliptin (N = 98) | Ertugliflozin 15 mg + Sitagliptin (N = 96)
Overall [N (%)] | 1 (1.0) | 6 (6.1) | 3 (3.1)
Severe [N (%)] | 0 (0.0) | 0 (0.0) | 2 (2.1)

Lower Limb Amputation

In a long-term cardiovascular outcomes study [see Clinical Studies (14.2)], in patients with type 2 diabetes mellitus and established cardiovascular disease, the occurrence of non-traumatic lower limb amputations was reported with event rates of 4.7, 5.7, and 6.0 events per 1,000 patient-years in the placebo, ertugliflozin 5 mg, and ertugliflozin 15 mg treatment arms, respectively.

Across seven ertugliflozin clinical trials, non-traumatic lower limb amputations were reported in 1 (0.1%) patient in the comparator group, 3 (0.2%) patients in the ertugliflozin 5 mg group, and 8 (0.5%) patients in the ertugliflozin 15 mg group.

Genital Mycotic Infections

In the pool of three placebo-controlled clinical trials, the incidence of female genital mycotic infections (e.g., genital candidiasis, genital infection fungal, vaginal infection, vulvitis, vulvovaginal candidiasis, vulvovaginal mycotic infection, vulvovaginitis) occurred in 3%, 9.1%, and 12.2% of females treated with placebo, ertugliflozin 5 mg, and ertugliflozin 15 mg, respectively (see Table 1). In females, discontinuation due to genital mycotic infections occurred in 0% and 0.6% of patients treated with placebo and ertugliflozin, respectively.

In the same pool, male genital mycotic infections (e.g., balanitis candida, balanoposthitis, genital infection, genital infection fungal) occurred in 0.4%, 3.7%, and 4.2% of males treated with placebo, ertugliflozin 5 mg, ertugliflozin 15 mg, respectively (see Table 1). Male genital mycotic infections occurred more commonly in uncircumcised males. In males, discontinuations due to genital mycotic infections occurred in 0% and 0.2% of patients treated with placebo and ertugliflozin, respectively. Phimosis was reported in 8 of 1,729 (0.5%) male ertugliflozin-treated patients, of which four required circumcision.

Urinary Tract Infections

In VERTIS CV, urinary tract infections (e.g., urinary tract infection, cystitis, dysuria) occurred in 10.2%, 12.2% and 12.0% of patients treated with placebo, ertugliflozin 5 mg and ertugliflozin 15 mg, respectively. The incidences of serious urinary tract infections were 0.8%, 0.9% and 0.4% with placebo, ertugliflozin 5 mg and ertugliflozin 15 mg, respectively.

Sitagliptin

The following additional adverse reactions have been reported in clinical studies with sitagliptin: upper respiratory tract infection, nasopharyngitis, headache, abdominal pain, nausea, diarrhea. In addition, in a study of sitagliptin as add-on combination therapy with metformin HCl and rosiglitazone, peripheral edema was noted with a higher incidence than placebo.

In a pooled analysis of the two monotherapy studies, the add-on to metformin HCl study, and the add-on to pioglitazone study, the overall incidence of adverse reactions of hypoglycemia was 1.2% in patients treated with sitagliptin 100 mg and 0.9% in patients treated with placebo. In the add-on to sulfonylurea and add-on to insulin studies, hypoglycemia was also more commonly reported in patients treated with sitagliptin compared to placebo. In the add-on to glimepiride (+/- metformin HCl) study, the overall incidence of hypoglycemia was 12.2% in patients treated with sitagliptin 100 mg and 1.8% in patients treated with placebo. In the add-on to insulin (+/- metformin HCl) study, the overall incidence of hypoglycemia was 15.5% in patients treated with sitagliptin 100 mg and 7.8% in patients treated with placebo. In all studies, adverse reactions of hypoglycemia were based on all reports of symptomatic hypoglycemia. A concurrent blood glucose measurement was not required although most (74%) reports of hypoglycemia were accompanied by a blood glucose measurement ≤70 mg/dL.

In a pooled analysis of 19 double-blind clinical trials that included data from 10,246 patients randomized to receive sitagliptin 100 mg/day (N=5,429) or corresponding (active or placebo) control (N=4,817), the incidence of non-adjudicated acute pancreatitis events was 0.1 per 100 patient-years in each group (4 patients with an event in 4,708 patient-years for sitagliptin and 4 patients with an event in 3,942 patient-years for control).

Laboratory Tests

Ertugliflozin

Changes in Serum Creatinine and eGFR

Initiation of ertugliflozin causes an increase in serum creatinine and decrease in eGFR within weeks of starting therapy and then these changes stabilize. In a study of patients with moderate renal impairment, larger mean changes were observed. In a long-term cardiovascular outcomes trial, an initial increase in serum creatinine and a decrease in eGFR within weeks of starting therapy was observed (at Week 6 eGFR changes of -2.7, -3.8 and -0.4 mL/min/1.73 m^2 in the ertugliflozin 5 mg, ertugliflozin 15 mg and placebo arms, respectively). The initial decline was followed by a recovery toward baseline to Week 52 (eGFR change from baseline of - 0.4, - 1.1 and - 0.2 mL/min/1.73 m^2 in ertugliflozin 5 mg, ertugliflozin 15 mg, and placebo arms, respectively). Acute hemodynamic changes may play a role in the early renal function changes observed with ertugliflozin since they are reversed after treatment discontinuation.

Increases in Low-Density Lipoprotein Cholesterol (LDL-C)

In the pool of three placebo-controlled trials, dose-related increases in LDL-C were observed in patients treated with ertugliflozin. Mean percent changes from baseline to Week 26 in LDL-C relative to placebo were 2.6% and 5.4% with ertugliflozin 5 mg and ertugliflozin 15 mg, respectively. The range of mean baseline LDL-C was 96.6 to 97.7 mg/dL across treatment groups.

Increases in Hemoglobin

In the pool of three placebo-controlled trials, mean changes (percent changes) from baseline to Week 26 in hemoglobin were -0.21 g/dL (-1.4%) with placebo, 0.46 g/dL (3.5%) with ertugliflozin 5 mg, and 0.48 g/dL (3.5%) with ertugliflozin 15 mg. The range of mean baseline hemoglobin was 13.90 to 14.00 g/dL across treatment groups. At the end of treatment, 0.0%, 0.2%, and 0.4% of patients treated with placebo, ertugliflozin 5 mg, and ertugliflozin 15 mg, respectively, had a hemoglobin increase greater than 2 g/dL and above the upper limit of normal.

Increases in Serum Phosphate

In the pool of three placebo-controlled trials, mean changes (percent changes) from baseline in serum phosphate were 0.04 mg/dL (1.9%) with placebo, 0.21 mg/dL (6.8%) with ertugliflozin 5 mg, and 0.26 mg/dL (8.5%) with ertugliflozin 15 mg. The range of mean baseline serum phosphate was 3.53 to 3.54 mg/dL across treatment groups. In a clinical trial of patients with moderate renal impairment, mean changes (percent changes) from baseline at Week 26 in serum phosphate were -0.01 mg/dL (0.8%) with placebo, 0.29 mg/dL (9.7%) with ertugliflozin 5 mg, and 0.24 mg/dL (7.8%) with ertugliflozin 15 mg.

Sitagliptin

Across clinical studies, the incidence of laboratory adverse reactions was similar in patients treated with sitagliptin 100 mg compared to patients treated with placebo. A small increase in white blood cell count (WBC) was observed due to an increase in neutrophils. This increase in WBC (of approximately 200 cells/microL vs. placebo, in four pooled placebo-controlled clinical studies, with a mean baseline WBC count of approximately 6,600 cells/microL) is not considered to be clinically relevant. In a 12-week study of 91 patients with chronic renal insufficiency, 37 patients with moderate renal insufficiency were randomized to sitagliptin 50 mg daily, while 14 patients with the same magnitude of renal impairment were randomized to placebo. Mean (SE) increases in serum creatinine were observed in patients treated with sitagliptin [0.12 mg/dL (0.04)] and in patients treated with placebo [0.07 mg/dL (0.07)]. The clinical significance of this added increase in serum creatinine relative to placebo is not known.

6.2 Postmarketing Experience

Additional adverse reactions have been identified during postapproval use of ertugliflozin or sitagliptin, both components of STEGLUJAN. Because these reactions are reported voluntarily from a population of uncertain size, it is generally not possible to reliably estimate their frequency or establish a causal relationship to drug exposure.

Ertugliflozin

- Infections: necrotizing fasciitis of the perineum (Fournier’s Gangrene)
- Skin and Subcutaneous Tissue Disorders: angioedema, rash

Sitagliptin

- Skin and Subcutaneous Tissue Disorders: hypersensitivity reactions including anaphylaxis, angioedema, rash, urticaria, cutaneous vasculitis, bullous pemphigoid, exfoliative skin conditions including Stevens-Johnson syndrome, and pruritus
- Investigations: hepatic enzyme elevations
- Gastrointestinal Disorders: acute pancreatitis, including fatal and non-fatal hemorrhagic and necrotizing pancreatitis, constipation, vomiting, mouth ulceration, and stomatitis
- Renal and Urinary Disorders: worsening renal function, including acute renal failure (sometimes requiring dialysis), and tubulointerstitial nephritis
- Musculoskeletal and Connective Tissue Disorders: severe and disabling arthralgia, myalgia, pain in extremity, back pain, and rhabdomyolysis
- Nervous System Disorders: headache

7 DRUG INTERACTIONS

Table 3: Clinically Significant Drug Interactions with STEGLUJAN
Insulin or Insulin Secretagogues
Clinical Impact: | The risk of hypoglycemia is increased when STEGLUJAN is used in combination with insulin or an insulin secretagogue.
Intervention: | A lower dose of insulin or insulin secretagogue may be required to minimize the risk of hypoglycemia when used in combination with STEGLUJAN.
Lithium
Clinical Impact: | Concomitant use of an SGLT2 inhibitor with lithium may decrease serum lithium concentrations.
Intervention: | Monitor serum lithium concentration more frequently during STEGLUJAN initiation and dosage changes.
Positive Urine Glucose Test
Clinical Impact: | SGLT2 inhibitors increase urinary glucose excretion and will lead to positive urine glucose tests.
Intervention: | Monitoring glycemic control with urine glucose tests is not recommended in patients taking SGLT2 inhibitors. Use alternative methods to monitor glycemic control.
Interference with 1,5-anhydroglucitol (1,5-AG) Assay
Clinical Impact: | Measurements of 1,5-AG are unreliable in assessing glycemic control in patients taking SGLT2 inhibitors.
Intervention: | Monitoring glycemic control with 1,5-AG assay is not recommended. Use alternative methods to monitor glycemic control.

8 USE IN SPECIFIC POPULATIONS

8.1 Pregnancy

Risk Summary

Based on animal data showing adverse renal effects, from ertugliflozin, STEGLUJAN is not recommended during the second and third trimesters of pregnancy.

The limited available data with ertugliflozin and sitagliptin use during pregnancy are not sufficient to determine a drug associated risk of adverse developmental outcomes. There are risks to the mother and fetus associated with poorly controlled diabetes in pregnancy (see Clinical Considerations).

In animal studies, adverse renal changes were observed in rats when ertugliflozin was administered during a period of renal development corresponding to the late second and third trimesters of human pregnancy. Doses approximately 13 times the maximum clinical dose caused renal pelvic and tubule dilatations and renal mineralization that were not fully reversible. There was no evidence of fetal harm in rats or rabbits at exposures of ertugliflozin approximately 300 times higher than the maximal clinical dose of 15 mg/day when administered during organogenesis (see Data).

In rats and rabbits, sitagliptin doses of 250 and 125 mg/kg, respectively (approximately 30 and 20 times the human exposure at the maximum recommended human dose) did not adversely affect development outcomes of either species.

The estimated background risk of major birth defects is 6-10% in women with pre-gestational diabetes with a HbA1c >7 and has been reported to be as high as 20-25% in women with HbA1c >10. The estimated background risk of miscarriage for the indicated population is unknown. In the U.S. general population, the estimated background risk of major birth defects and miscarriage in clinically recognized pregnancies is 2-4% and 15-20%, respectively.

Clinical Considerations

Disease-Associated Maternal and/or Embryo/Fetal Risk

Poorly controlled diabetes in pregnancy increases the maternal risk for diabetic ketoacidosis, pre-eclampsia, spontaneous abortions, preterm delivery, and delivery complications. Poorly controlled diabetes increases the fetal risk for major birth defects, stillbirth, and macrosomia related morbidity.

Data

Animal Data

Ertugliflozin

When ertugliflozin was orally administered to juvenile rats from PND 21 to PND 90, increased kidney weight, renal tubule and renal pelvis dilatation, and renal mineralization occurred at doses greater than or equal to 5 mg/kg (13-fold human exposures, based on AUC). These effects occurred with drug exposure during periods of renal development in rats that correspond to the late second and third trimester of human renal development, and did not fully reverse within a 1-month recovery period.

In embryo-fetal development studies, ertugliflozin (50, 100 and 250 mg/kg/day) was administered orally to rats on gestation days 6 to 17 and to rabbits on gestation days 7 to 19. Ertugliflozin did not adversely affect developmental outcomes in rats and rabbits at maternal exposures that were approximately 300 times the human exposure at the maximum clinical dose of 15 mg/day, based on AUC. A maternally toxic dose (250 mg/kg/day) in rats (707 times the clinical dose) was associated with reduced fetal viability, and a higher incidence of a visceral malformation (membranous ventricular septal defect). In the pre- and post-natal development study in pregnant rats, ertugliflozin was administered to the dams from gestation day 6 through lactation day 21 (weaning). Decreased post-natal growth (weight gain) was observed at maternal doses ≥100 mg/kg/day (greater than or equal to 331 times the human exposure at the maximum clinical dose of 15 mg/day, based on AUC).

Sitagliptin

Sitagliptin administered to pregnant female rats and rabbits from gestation day 6 to 20 (organogenesis) did not adversely affect developmental outcomes at oral doses up to 250 mg/kg (rats) and 125 mg/kg (rabbits), or approximately 30 and 20 times human exposure at the maximum recommended human dose (MRHD) of 100 mg/day based on AUC comparisons. Higher doses increased the incidence of rib malformations in offspring at 1,000 mg/kg, or approximately 100 times human exposure at the MRHD.

Sitagliptin administered to female rats from gestation day 6 to lactation day 21 decreased body weight in male and female offspring at 1,000 mg/kg. No functional or behavioral toxicity was observed in offspring of rats.

Placental transfer of sitagliptin administered to pregnant rats was approximately 45% at 2 hours and 80% at 24 hours postdose. Placental transfer of sitagliptin administered to pregnant rabbits was approximately 66% at 2 hours and 30% at 24 hours.

8.2 Lactation

Risk Summary

There is no information regarding the presence of STEGLUJAN, in human milk, the effects on the breastfed infant, or the effects on milk production. Ertugliflozin and sitagliptin are present in the milk of lactating rats (see Data). Since human kidney maturation occurs in utero and during the first 2 years of life when lactational exposure may occur, there may be risk to the developing human kidney, based on data with ertugliflozin. Because of the potential for serious adverse reactions in a breastfed infant, advise women that the use of STEGLUJAN is not recommended while breastfeeding.

Data

Ertugliflozin

The lacteal excretion of radiolabeled ertugliflozin in lactating rats was evaluated 10 to 12 days after parturition. Ertugliflozin-derived radioactivity exposure in milk and plasma were similar, with a milk/plasma ratio of 1.07, based on AUC. Juvenile rats directly exposed to ertugliflozin during a developmental period corresponding to human kidney maturation were associated with a risk to the developing kidney (persistent increased organ weight, renal mineralization, and renal pelvic and tubular dilatations).

Sitagliptin

Sitagliptin is secreted in the milk of lactating rats at a milk to plasma ratio of 4:1.

8.4 Pediatric Use

Safety and effectiveness of STEGLUJAN in pediatric patients under 18 years of age have not been established.

8.5 Geriatric Use

STEGLUJAN

No dosage adjustment of STEGLUJAN is recommended based on age. Elderly patients are more likely to have decreased renal function. Because renal function abnormalities can occur after initiating ertugliflozin, and sitagliptin is known to be substantially excreted by the kidneys, renal function should be assessed more frequently in elderly patients [see Dosage and Administration (2.1) and Warnings and Precautions (5.4)].

Ertugliflozin

In ertugliflozin clinical trials, a total of 876 (25.7%) patients treated with ertugliflozin were 65 years and older, and 152 (4.5%) patients treated with ertugliflozin were 75 years and older. Patients 65 years and older had a higher incidence of adverse reactions related to volume depletion compared to younger patients; events were reported in 1.1%, 2.2%, and 2.6% of patients treated with comparator, ertugliflozin 5 mg, and ertugliflozin 15 mg, respectively [see Warnings and Precautions (5.5) and Adverse Reactions (6.1)].

In VERTIS CV, a total of 2780 (50.5%) patients treated with ertugliflozin were 65 years and older, and 595 (10.8%) patients treated with ertugliflozin were 75 years and older. Safety and efficacy were generally similar for patients age 65 years and older compared to patients younger than 65.

Sitagliptin

Of the total number of subjects (N=3,884) in pre-approval clinical safety and efficacy studies of sitagliptin, 725 patients were 65 years and over, while 61 patients were 75 years and over. No overall differences in safety or effectiveness were observed between subjects 65 years and over and younger subjects. While this and other reported clinical experience have not identified differences in responses between the elderly and younger patients, greater sensitivity of some older individuals cannot be ruled out.

8.6 Renal Impairment

A 26-week placebo-controlled study of 313 patients with Stage 3 Chronic Kidney Disease (eGFR ≥30 to less than 60 mL/min/1.73 m^2) treated with ertugliflozin did not demonstrate improvement in glycemic control. In the VERTIS CV study, there were 1370 patients (25%) with an eGFR ≥90 mL/min/1.73 m^2, 2929 patients (53%) with an eGFR of ≥60 to less than 90 mL/min/1.73 m^2, 879 patients (16%) with an eGFR of ≥45 to less than 60 mL/min/1.73 m^2 and 299 patients (5%) with eGFR of 30 to <45 mL/min/1.73 m^2 treated with ertugliflozin. Similar effects on glycemic control at Week 18 were observed in patients treated with ertugliflozin in each eGFR subgroup and also in the overall patient population.

STEGLUJAN is contraindicated in patients with severe renal impairment (eGFR less than 30 mL/min/1.73 m^2), ESRD, or on dialysis [see Contraindications (4)].

No dosage adjustment is needed in patients with eGFR ≥45 mL/min/1.73 m^2.

8.7 Hepatic Impairment

No dosage adjustment of STEGLUJAN is necessary in patients with mild or moderate hepatic impairment. STEGLUJAN has not been studied in patients with severe hepatic impairment and is not recommended for use in this patient population [see Clinical Pharmacology (12.3)].

10 OVERDOSAGE

STEGLUJAN

In the event of an overdose with STEGLUJAN, contact the Poison Help line (1-800-222-1222) or a medical toxicologist for additional overdosage management recommendations. Employ the usual supportive measures as dictated by the patient's clinical status.

Ertugliflozin

Removal of ertugliflozin by hemodialysis has not been studied.

Sitagliptin

In the event of an overdose, it is reasonable to employ the usual supportive measures, e.g., remove unabsorbed material from the gastrointestinal tract, employ clinical monitoring (including obtaining an electrocardiogram), and institute supportive therapy as dictated by the patient's clinical status.

Sitagliptin is modestly dialyzable. In clinical studies, approximately 13.5% of the dose was removed over a 3- to 4-hour hemodialysis session. Prolonged hemodialysis may be considered if clinically appropriate. It is not known if sitagliptin is dialyzable by peritoneal dialysis.

11 DESCRIPTION

STEGLUJAN (ertugliflozin and sitagliptin) tablet for oral use contains ertugliflozin L-pyroglutamic acid, a SGLT2 inhibitor, and sitagliptin phosphate, a DPP-4 inhibitor.

Ertugliflozin

The chemical name of ertugliflozin L-pyroglutamic acid is (1S,2S,3S,4R,5S)-5-(4-chloro-3-(4-ethoxybenzyl)phenyl)-1-(hydroxymethyl)-6,8-dioxabicyclo[3.2.1]octane-2,3,4-triol, compound with (2S)-5-oxopyrrolidine-2-carboxylic acid. The molecular formula is C27H32ClNO10 and the molecular weight is 566.00.

The chemical structure is:

Ertugliflozin L-pyroglutamic acid is a white to off-white powder that is soluble in ethyl alcohol and acetone, slightly soluble in ethyl acetate and acetonitrile and very slightly soluble in water.

Sitagliptin

Sitagliptin phosphate monohydrate is described chemically as 7-[(3R)-3-amino-1-oxo-4-(2,4,5-trifluorophenyl)butyl]-5,6,7,8-tetrahydro-3-(trifluoromethyl)-1,2,4-triazolo[4,3-a]pyrazine phosphate (1:1) monohydrate.

The empirical formula is C16H15F6N5O∙H3PO4∙H2O and the molecular weight is 523.32. The structural formula is:

Sitagliptin phosphate monohydrate is a white to off-white, crystalline, non-hygroscopic powder. It is soluble in water and N,N-dimethyl formamide; slightly soluble in methanol; very slightly soluble in ethanol, acetone, and acetonitrile; and insoluble in isopropanol and isopropyl acetate.

STEGLUJAN is available for oral use as film-coated tablets containing:

- 6.48 mg ertugliflozin L-pyroglutamic acid equivalent to 5 mg of ertugliflozin and 128.5 mg sitagliptin phosphate monohydrate equivalent to 100 mg sitagliptin (STEGLUJAN 5/100)
- 19.43 mg ertugliflozin L-pyroglutamic acid equivalent to 15 mg of ertugliflozin and 128.5 mg sitagliptin phosphate monohydrate equivalent to 100 mg sitagliptin (STEGLUJAN 15/100)

Inactive ingredients are microcrystalline cellulose, dibasic calcium phosphate anhydrous, croscarmellose sodium, sodium stearyl fumarate, magnesium stearate, and propyl gallate.

The film coating contains: hypromellose, hydroxypropyl cellulose, titanium dioxide, iron oxide red, iron oxide yellow, ferrosoferric oxide/black iron oxide, and carnauba wax.

12 CLINICAL PHARMACOLOGY

12.1 Mechanism of Action

STEGLUJAN

STEGLUJAN combines two antihyperglycemic agents with complementary mechanisms of action to improve glycemic control in patients with type 2 diabetes mellitus: ertugliflozin, a SGLT2 inhibitor, and sitagliptin, a DPP-4 inhibitor.

Ertugliflozin

SGLT2 is the predominant transporter responsible for reabsorption of glucose from the glomerular filtrate back into the circulation. Ertugliflozin is an inhibitor of SGLT2. By inhibiting SGLT2, ertugliflozin reduces renal reabsorption of filtered glucose and lowers the renal threshold for glucose, and thereby increases urinary glucose excretion.

Sitagliptin

Sitagliptin is a DPP-4 inhibitor, which is believed to exert its actions in patients with type 2 diabetes mellitus by slowing the inactivation of incretin hormones. Concentrations of the active intact hormones are increased by sitagliptin, thereby increasing and prolonging the action of these hormones. Incretin hormones, including glucagon-like peptide-1 (GLP-1) and glucose-dependent insulinotropic polypeptide (GIP), are released by the intestine throughout the day, and levels are increased in response to a meal. These hormones are rapidly inactivated by the enzyme, DPP-4. The incretins are part of an endogenous system involved in the physiologic regulation of glucose homeostasis. When blood glucose concentrations are normal or elevated, GLP-1 and GIP increase insulin synthesis and release from pancreatic beta cells by intracellular signaling pathways involving cyclic AMP. GLP-1 also lowers glucagon secretion from pancreatic alpha cells, leading to reduced hepatic glucose production. By increasing and prolonging active incretin levels, sitagliptin increases insulin release and decreases glucagon levels in the circulation in a glucose-dependent manner. Sitagliptin demonstrates selectivity for DPP-4 and does not inhibit DPP-8 or DPP-9 activity in vitro at concentrations approximating those from therapeutic doses.

12.2 Pharmacodynamics

Ertugliflozin

Urinary Glucose Excretion and Urinary Volume

Dose-dependent increases in the amount of glucose excreted in urine were observed in healthy subjects and in patients with type 2 diabetes mellitus following single- and multiple-dose administration of ertugliflozin. Dose-response modeling indicates that ertugliflozin 5 mg and 15 mg result in near maximal urinary glucose excretion (UGE). Enhanced UGE is maintained after multiple-dose administration. UGE with ertugliflozin also results in increases in urinary volume.

Cardiac Electrophysiology

The effect of ertugliflozin on QTc interval was evaluated in a Phase 1 randomized, placebo- and positive-controlled 3-period crossover study in 42 healthy subjects. At 6.7 times the therapeutic exposures with maximum recommended dose, ertugliflozin does not prolong QTc to any clinically relevant extent.

Sitagliptin

General

In patients with type 2 diabetes mellitus, administration of sitagliptin led to inhibition of DPP-4 enzyme activity for a 24-hour period. After an oral glucose load or a meal, this DPP-4 inhibition resulted in a 2- to 3-fold increase in circulating levels of active GLP-1 and GIP, decreased glucagon concentrations, and increased responsiveness of insulin release to glucose, resulting in higher C-peptide and insulin concentrations. The rise in insulin with the decrease in glucagon was associated with lower fasting glucose concentrations and reduced glucose excursion following an oral glucose load or a meal.

In a two-day study in healthy subjects, sitagliptin alone increased active GLP-1 concentrations, whereas metformin alone increased active and total GLP-1 concentrations to similar extents. Coadministration of sitagliptin and metformin had an additive effect on active GLP-1 concentrations. Sitagliptin, but not metformin, increased active GIP concentrations. It is unclear how these findings relate to changes in glycemic control in patients with type 2 diabetes mellitus.

In studies with healthy subjects, sitagliptin did not lower blood glucose or cause hypoglycemia.

Cardiac Electrophysiology

In a randomized, placebo controlled crossover study, 79 healthy subjects were administered a single oral dose of sitagliptin 100 mg, sitagliptin 800 mg (8 times the recommended dose), and placebo. At the recommended dose of 100 mg, there was no effect on the QTc interval obtained at the peak plasma concentration, or at any other time during the study. Following the 800 mg dose, the maximum increase in the placebo corrected mean change in QTc from baseline was observed at 3 hours postdose and was 8.0 msec. This increase is not considered to be clinically significant. At the 800 mg dose, peak sitagliptin plasma concentrations were approximately 11 times higher than the peak concentrations following a 100-mg dose.

In patients with type 2 diabetes mellitus administered sitagliptin 100 mg (N=81) or sitagliptin 200 mg (N=63) daily, there were no meaningful changes in QTc interval based on ECG data obtained at the time of expected peak plasma concentration.

12.3 Pharmacokinetics

General Introduction

Ertugliflozin

The pharmacokinetics of ertugliflozin are similar in healthy subjects and patients with type 2 diabetes mellitus. The steady state mean plasma AUC and Cmax were 398 ng∙hr/mL and 81.3 ng/mL, respectively, with 5 mg ertugliflozin once daily treatment, and 1,193 ng∙hr/mL and 268 ng/mL, respectively, with 15 mg ertugliflozin once daily treatment. Steady-state is reached after 4 to 6 days of once-daily dosing with ertugliflozin. Ertugliflozin does not exhibit time-dependent pharmacokinetics and accumulates in plasma up to 10-40% following multiple dosing.

Sitagliptin

The pharmacokinetics of sitagliptin have been extensively characterized in healthy subjects and patients with type 2 diabetes mellitus. After oral administration of a 100-mg dose to healthy subjects, sitagliptin was rapidly absorbed, with peak plasma concentrations (median Tmax) occurring 1 to 4 hours postdose. Plasma AUC of sitagliptin increased in a dose proportional manner. Following a single oral 100-mg dose to healthy volunteers, mean plasma AUC of sitagliptin was 8.52 µM∙hr, Cmax was 950 nM, and apparent terminal half-life (t1/2) was 12.4 hours. Plasma AUC of sitagliptin increased approximately 14% following 100-mg doses at steady state compared to the first dose. The intra subject and inter subject coefficients of variation for sitagliptin AUC were small (5.8% and 15.1%). The pharmacokinetics of sitagliptin was generally similar in healthy subjects and in patients with type 2 diabetes mellitus.

Absorption

STEGLUJAN

The effects of a high-fat meal on the pharmacokinetics of ertugliflozin and sitagliptin when administered as STEGLUJAN tablets are comparable to those reported for the individual tablets. Administration of STEGLUJAN with food decreased ertugliflozin Cmax by 29% and had no meaningful effect on ertugliflozin AUCinf, and on sitagliptin AUCinf and Cmax.

Ertugliflozin

Following single-dose oral administration of 5 mg and 15 mg of ertugliflozin, peak plasma concentrations of ertugliflozin occur at 1 hour postdose (median Tmax) under fasted conditions. Plasma Cmax and AUC of ertugliflozin increase in a dose-proportional manner following single doses from 0.5 mg (0.1 times the lowest recommended dose) to 300 mg (20 times the highest recommended dose) and following multiple doses from 1 mg (0.2 times the lowest recommended dose) to 100 mg (6.7 times the highest recommended dose). The absolute oral bioavailability of ertugliflozin following administration of a 15 mg dose is approximately 100%.

Effect of Food

Administration of ertugliflozin with a high-fat and high-calorie meal decreases ertugliflozin Cmax by 29% and prolongs Tmax by 1 hour, but does not alter AUC as compared with the fasted state. The observed effect of food on ertugliflozin pharmacokinetics is not considered clinically relevant, and ertugliflozin may be administered with or without food. In Phase 3 clinical trials, ertugliflozin was administered without regard to meals.

Sitagliptin

The absolute bioavailability of sitagliptin is approximately 87%. Because coadministration of a high fat meal with sitagliptin had no effect on the pharmacokinetics, sitagliptin may be administered with or without food.

Distribution

Ertugliflozin

The mean steady-state volume of distribution of ertugliflozin following an intravenous dose is 85.5 L. Plasma protein binding of ertugliflozin is 93.6% and is independent of ertugliflozin plasma concentrations. Plasma protein binding is not meaningfully altered in patients with renal or hepatic impairment. The blood-to-plasma concentration ratio of ertugliflozin is 0.66.

Sitagliptin

The mean volume of distribution at steady state following a single 100-mg intravenous dose of sitagliptin to healthy subjects is approximately 198 L. The fraction of sitagliptin reversibly bound to plasma proteins is low (38%).

Elimination

Metabolism

Ertugliflozin

Metabolism is the primary clearance mechanism for ertugliflozin. The major metabolic pathway for ertugliflozin is UGT1A9 and UGT2B7-mediated O-glucuronidation to two glucuronides that are pharmacologically inactive at clinically relevant concentrations. CYP-mediated (oxidative) metabolism of ertugliflozin is minimal (12%).

Sitagliptin

Approximately 79% of sitagliptin is excreted unchanged in the urine with metabolism being a minor pathway of elimination.

Following a [^14C]sitagliptin oral dose, approximately 16% of the radioactivity was excreted as metabolites of sitagliptin. Six metabolites were detected at trace levels and are not expected to contribute to the plasma DPP-4 inhibitory activity of sitagliptin. In vitro studies indicated that the primary enzyme responsible for the limited metabolism of sitagliptin was CYP3A4, with contribution from CYP2C8.

Excretion

Ertugliflozin

The mean systemic plasma clearance following an intravenous 100 µg dose was 11.2 L/hr. The mean elimination half-life in type 2 diabetic patients with normal renal function was estimated to be 16.6 hours based on the population pharmacokinetic analysis. Following administration of an oral [^14C]-ertugliflozin solution to healthy subjects, approximately 40.9% and 50.2% of the drug-related radioactivity was eliminated in feces and urine, respectively. Only 1.5% of the administered dose was excreted as unchanged ertugliflozin in urine and 33.8% as unchanged ertugliflozin in feces, which is likely due to biliary excretion of glucuronide metabolites and subsequent hydrolysis to parent.

Sitagliptin

Following administration of an oral [^14C]sitagliptin dose to healthy subjects, approximately 100% of the administered radioactivity was eliminated in feces (13%) or urine (87%) within one week of dosing. The apparent terminal t1/2 following a 100-mg oral dose of sitagliptin was approximately 12.4 hours and renal clearance was approximately 350 mL/min.

Elimination of sitagliptin occurs primarily via renal excretion and involves active tubular secretion. Sitagliptin is a substrate for human organic anion transporter-3 (hOAT-3), which may be involved in the renal elimination of sitagliptin. The clinical relevance of hOAT-3 in sitagliptin transport has not been established. Sitagliptin is also a substrate of p-glycoprotein, which may also be involved in mediating the renal elimination of sitagliptin. However, cyclosporine, a p-glycoprotein inhibitor, did not reduce the renal clearance of sitagliptin.

Specific Populations

Patients with Renal Impairment

STEGLUJAN

Studies characterizing the pharmacokinetics of ertugliflozin and sitagliptin after administration of STEGLUJAN in renally impaired patients have not been performed [see Dosage and Administration (2.1)].

Ertugliflozin

In a clinical pharmacology study in patients with type 2 diabetes mellitus and mild, moderate, or severe renal impairment (as determined by eGFR), following a single-dose administration of 15 mg ertugliflozin, the mean increases in AUC of ertugliflozin were 1.6-, 1.7-, and 1.6-fold, respectively, for mild, moderate and severe renally-impaired patients, compared to subjects with normal renal function. These increases in ertugliflozin AUC are not considered clinically meaningful. The 24-hour urinary glucose excretion declined with increasing severity of renal impairment [see Warnings and Precautions (5.4) and Use in Specific Populations (8.6)]. The plasma protein binding of ertugliflozin was unaffected in patients with renal impairment.

Sitagliptin

An approximately 2-fold increase in the plasma AUC of sitagliptin was observed in patients with moderate renal impairment with eGFR of 30 to less than 45 mL/min/1.73 m^2, and an approximately 4-fold increase was observed in patients with severe renal impairment, including patients with ESRD on hemodialysis, as compared to normal healthy control subjects.

Patients with Hepatic Impairment

Ertugliflozin

Moderate hepatic impairment (based on the Child-Pugh classification) did not result in an increase in exposure of ertugliflozin. The AUC of ertugliflozin decreased by approximately 13%, and Cmax decreased by approximately 21% compared to subjects with normal hepatic function. This decrease in ertugliflozin exposure is not considered clinically meaningful. There is no clinical experience in patients with Child-Pugh class C (severe) hepatic impairment. The plasma protein binding of ertugliflozin was unaffected in patients with moderate hepatic impairment [see Use in Specific Populations (8.7)].

Sitagliptin

In patients with moderate hepatic insufficiency (Child Pugh score 7 to 9), mean AUC and Cmax of sitagliptin increased approximately 21% and 13%, respectively, compared to healthy matched controls following administration of a single 100-mg dose of sitagliptin. These differences are not considered to be clinically meaningful. No dosage adjustment for sitagliptin is necessary for patients with mild or moderate hepatic insufficiency.

There is no clinical experience in patients with severe hepatic insufficiency (Child Pugh score >9) [see Use in Specific Populations (8.7)].

Effects of Age, Body Weight/ Body Mass Index (BMI), Gender, and Race

Ertugliflozin

Based on a population pharmacokinetic analysis, age, body weight, gender, and race do not have a clinically meaningful effect on the pharmacokinetics of ertugliflozin.

Sitagliptin

Based on a population pharmacokinetic analysis or a composite analysis of available pharmacokinetic data, BMI, gender, and race do not have a clinically meaningful effect on the pharmacokinetics of sitagliptin. When the effects of age on renal function are taken into account, age alone did not have a clinically meaningful impact on the pharmacokinetics of sitagliptin based on a population pharmacokinetic analysis. Elderly subjects (65 to 80 years) had approximately 19% higher plasma concentrations of sitagliptin compared to younger subjects.

Drug Interaction Studies

STEGLUJAN

Coadministration of single dose of ertugliflozin (15 mg) and sitagliptin (100 mg) did not meaningfully alter the pharmacokinetics of either ertugliflozin or metformin in healthy subjects.

Pharmacokinetic drug interaction studies with STEGLUJAN have not been performed; however, such studies have been conducted with ertugliflozin and sitagliptin, the individual components of STEGLUJAN.

Ertugliflozin

In Vitro Assessment of Drug Interactions

In in vitro studies, ertugliflozin and ertugliflozin glucuronides did not inhibit CYP450 isoenzymes (CYPs) 1A2, 2C9, 2C19, 2C8, 2B6, 2D6, or 3A4, and did not induce CYPs 1A2, 2B6, or 3A4. Ertugliflozin was not a time-dependent inhibitor of CYP3A in vitro. Ertugliflozin did not inhibit UGT1A6, 1A9, or 2B7 in vitro and was a weak inhibitor (IC50 >39 µM) of UGT1A1 and 1A4. Ertugliflozin glucuronides did not inhibit UGT1A1, 1A4, 1A6, 1A9, or 2B7 in vitro. Overall, ertugliflozin is unlikely to affect the pharmacokinetics of drugs eliminated by these enzymes. Ertugliflozin is a substrate of P-glycoprotein (P-gp) and breast cancer resistance protein (BCRP) transporters and is not a substrate of organic anion transporters (OAT1, OAT3), organic cation transporters (OCT1, OCT2), or organic anion transporting polypeptides (OATP1B1, OATP1B3). Ertugliflozin or ertugliflozin glucuronides do not meaningfully inhibit P-gp, OCT2, OAT1, or OAT3 transporters, or transporting polypeptides OATP1B1 and OATP1B3, at clinically relevant concentrations. Overall, ertugliflozin is unlikely to affect the pharmacokinetics of concurrently administered medications that are substrates of these transporters.

In Vivo Assessment of Drug Interactions

No dose adjustment of STEGLUJAN is recommended when coadministered with commonly prescribed medicinal products. Ertugliflozin pharmacokinetics were similar with and without coadministration of metformin, glimepiride, sitagliptin, and simvastatin in healthy subjects (see Figure 1). Coadministration of ertugliflozin with multiple doses of 600 mg once daily rifampin (an inducer of UGT and CYP enzymes) resulted in approximately 39% and 15% mean reductions in ertugliflozin AUC and Cmax, respectively, relative to ertugliflozin administered alone. These changes in exposure are not considered clinically relevant. Ertugliflozin had no clinically relevant effect on the pharmacokinetics of metformin, glimepiride, sitagliptin, and simvastatin when coadministered in healthy subjects (see Figure 2). Physiologically-based PK (PBPK) modeling suggests that coadministration of mefenamic acid (UGT inhibitor) may increase the AUC and Cmax of ertugliflozin by 1.51- and 1.19-fold, respectively. These predicted changes in exposure are not considered clinically relevant.

Figure 1: Effects of Other Drugs on the Pharmacokinetics of Ertugliflozin

Figure 2: Effects of Ertugliflozin on the Pharmacokinetics of Other Drugs

Sitagliptin

In Vitro Assessment of Drug Interactions

Sitagliptin is not an inhibitor of CYP isozymes CYP3A4, 2C8, 2C9, 2D6, 1A2, 2C19 or 2B6, and is not an inducer of CYP3A4. Sitagliptin is a p-glycoprotein substrate, but does not inhibit p-glycoprotein mediated transport of digoxin. Based on these results, sitagliptin is considered unlikely to cause interactions with other drugs that utilize these pathways.

Sitagliptin is not extensively bound to plasma proteins. Therefore, the propensity of sitagliptin to be involved in clinically meaningful drug-drug interactions mediated by plasma protein binding displacement is very low.

In Vivo Assessment of Drug Interactions

Table 4: Effect of Coadministered Drugs on Systemic Exposure of Sitagliptin
Coadministered Drug | Dose of Coadministered Drug [All doses administered as single dose unless otherwise specified.] | Dose of Sitagliptin | Geometric Mean Ratio (ratio with/without coadministered drug) No Effect = 1.00
 |  |  |  | AUC [AUC is reported as AUC0-∞ unless otherwise specified.] | Cmax
No dosing adjustments required for the following:
Cyclosporine | 600 mg once daily | 100 mg once daily | Sitagliptin | 1.29 | 1.68
Metformin | 1,000 mg [Multiple dose.] twice daily for 14 days | 50 mg twice daily for 7 days | Sitagliptin | 1.02 [AUC0-12hr.] | 1.05

Table 5: Effect of Sitagliptin on Systemic Exposure of Coadministered Drugs
Coadministered Drug | Dose of Coadministered Drug [All doses administered as single dose unless otherwise specified. The 200 mg dose is 2 times the maximum recommended daily dose of sitagliptin.] | Dose of Sitagliptin | Geometric Mean Ratio (ratio with/without sitagliptin) No Effect = 1.00
 |  |  |  | AUC [AUC is reported as AUC0-∞ unless otherwise specified.] | Cmax
No dosing adjustments required for the following:
Digoxin | 0.25 mg [Multiple dose.] once daily for 10 days | 100 mg once daily for 10 days | Digoxin | 1.11 [AUC0-24hr.] | 1.18
Glyburide | 1.25 mg | 200 mg once daily for 6 days | Glyburide | 1.09 | 1.01
Simvastatin | 20 mg | 200 mg once daily for 5 days | Simvastatin | 0.85 [AUC0-last.] | 0.80
Simvastatin | 20 mg | 200 mg once daily for 5 days | Simvastatin Acid | 1.12 | 1.06
Rosiglitazone | 4 mg | 200 mg once daily for 5 days | Rosiglitazone | 0.98 | 0.99
Warfarin | 30 mg single dose on day 5 | 200 mg once daily for 11 days | S(-) Warfarin | 0.95 | 0.89
Warfarin | 30 mg single dose on day 5 | 200 mg once daily for 11 days | R(+) Warfarin | 0.99 | 0.89
Ethinyl estradiol and norethindrone | 21 days once daily of 35 µg ethinyl estradiol with norethindrone 0.5 mg × 7 days, 0.75 mg × 7 days, 1.0 mg × 7 days | 200 mg once daily for 21 days | Ethinyl estradiol | 0.99 | 0.97
Ethinyl estradiol and norethindrone | 21 days once daily of 35 µg ethinyl estradiol with norethindrone 0.5 mg × 7 days, 0.75 mg × 7 days, 1.0 mg × 7 days | 200 mg once daily for 21 days | Norethindrone | 1.03 | 0.98
Metformin | 1,000 mg twice daily for 14 days | 50 mg twice daily for 7 days | Metformin | 1.02 [AUC0-12hr.] | 0.97

13 NONCLINICAL TOXICOLOGY

13.1 Carcinogenesis, Mutagenesis, Impairment of Fertility

Carcinogenesis

Ertugliflozin

Carcinogenicity was evaluated in CD-1 mice and Sprague-Dawley rats. In the mouse study, ertugliflozin was administered by oral gavage at doses of 5, 15, and 40 mg/kg/day for up to 97 weeks in males and 102 weeks in females. There were no ertugliflozin-related neoplastic findings at doses up to 40 mg/kg/day (approximately 50 times human exposure at the maximum recommended human dose [MRHD] of 15 mg/day based on AUC). In the rat study, ertugliflozin was administered by oral gavage at doses of 1.5, 5, and 15 mg/kg/day for up to 92 weeks in females and 104 weeks in males. Ertugliflozin-related neoplastic findings included an increased incidence of adrenal medullary pheochromocytoma (PCC) in male rats at 15 mg/kg/day. Although the molecular mechanism remains unknown, this finding may be related to carbohydrate malabsorption leading to altered calcium homeostasis, which has been associated with PCC development in rats and has unclear relevance to human risk. The no-observed-effect level (NOEL) for neoplasia was 5 mg/kg/day (approximately 16 times human exposure at the MRHD of 15 mg/day, based on AUC).

Sitagliptin

A two year carcinogenicity study was conducted in male and female rats given oral doses of sitagliptin of 50, 150, and 500 mg/kg/day. There was an increased incidence of combined liver adenoma/carcinoma in males and females and of liver carcinoma in females at 500 mg/kg. This dose results in exposures approximately 60 times the human exposure at the maximum recommended daily adult human dose (MRHD) of 100 mg/day based on AUC comparisons. Liver tumors were not observed at 150 mg/kg, approximately 20 times the human exposure at the MRHD.

A two year carcinogenicity study was conducted in male and female mice given oral doses of sitagliptin of 50, 125, 250, and 500 mg/kg/day. There was no increase in the incidence of tumors in any organ up to 500 mg/kg, approximately 70 times human exposure at the MRHD.

Mutagenesis

Ertugliflozin

Ertugliflozin was not mutagenic or clastogenic with or without metabolic activation in the microbial reverse mutation, in vitro cytogenetic (human lymphocytes), and in vivo rat micronucleus assays.

Sitagliptin

Sitagliptin was not mutagenic or clastogenic with or without metabolic activation in the Ames bacterial mutagenicity assay, a Chinese hamster ovary (CHO) chromosome aberration assay, an in vitro cytogenetics assay in CHO, an in vitro rat hepatocyte DNA alkaline elution assay, and an in vivo micronucleus assay.

Impairment of Fertility

Ertugliflozin

In the rat fertility and embryonic development study, male and female rats were administered ertugliflozin at 5, 25, and 250 mg/kg/day. No effects on fertility were observed at 250 mg/kg/day (approximately 480 and 570 times male and female human exposures, respectively, at the MRHD of 15 mg/day based on AUC comparison).

Sitagliptin

In rat fertility studies with oral gavage doses of 125, 250, and 1,000 mg/kg, males were treated for 4 weeks prior to mating, during mating, up to scheduled termination (approximately 8 weeks total) and females were treated 2 weeks prior to mating through gestation day 7. No adverse effect on fertility was observed at 125 mg/kg (approximately 12 times human exposure at the MRHD of 100 mg/day based on AUC comparisons). At higher doses, nondose-related increased resorptions in females were observed (approximately 25 and 100 times human exposure at the MRHD based on AUC comparison).

14 CLINICAL STUDIES

14.1 Glycemic Control Trials in Patients with Type 2 Diabetes Mellitus

The efficacy and safety of ertugliflozin in combination with sitagliptin have been studied in 3 multi-center, randomized, double-blind, placebo- and active comparator-controlled, clinical studies involving 1,985 patients with type 2 diabetes mellitus. These studies included White, Hispanic or Latino, Black or African American, Asian, and other racial and ethnic groups, and patients with an age range of 21 to 85 years.

In patients with type 2 diabetes mellitus, treatment with ertugliflozin in combination with sitagliptin reduced HbA1c compared to placebo or active comparator.

In patients with type 2 diabetes mellitus treated with ertugliflozin in combination with sitagliptin, the change in HbA1c was generally similar across subgroups defined by age, sex, and race.

In Combination with Sitagliptin versus Ertugliflozin Alone and Sitagliptin Alone, as Add-on to Metformin HCl

A total of 1,233 patients with type 2 diabetes mellitus with inadequate glycemic control (HbA1c between 7.5% and 11%) on metformin HCl monotherapy (≥1,500 mg/day for ≥8 weeks) participated in a randomized, double-blind, 26-week, active controlled study (NCT02099110) to evaluate the efficacy and safety of ertugliflozin 5 mg or 15 mg administered orally in combination with sitagliptin 100 mg compared to the individual components. Patients were randomized to one of five treatment arms: ertugliflozin 5 mg, ertugliflozin 15 mg, sitagliptin 100 mg, ertugliflozin 5 mg + sitagliptin 100 mg, or ertugliflozin 15 mg + sitagliptin 100 mg.

At Week 26, ertugliflozin 5 mg or 15 mg + sitagliptin 100 mg provided statistically significantly greater reductions in HbA1c compared to the individual components. More patients achieved an HbA1c < 7% on the combination as compared to the individual components (see Table 6 and Figure 3).

Table 6: Results at Week 26 from a Factorial Study with Ertugliflozin and Sitagliptin as Add-on Combination Therapy with Metformin HCl Compared to Individual Components Alone [N includes all randomized and treated patients with a baseline measurement of the outcome variable. At Week 26 the primary HbA1c endpoint was missing for 13%, 10%, 11%, 11%, and 12% of patients and during the trial rescue medication was initiated by 6%, 6%, 3%, 2%, and 0% of patients randomized to sitagliptin, ertugliflozin 5 mg, ertugliflozin 15 mg, ertugliflozin 5 mg + sitagliptin, and ertugliflozin 15 mg + sitagliptin, respectively. Missing Week 26 measurements were imputed using multiple imputation with a mean equal to the baseline value of the patient. Results included measurements collected after initiation of rescue medication. For those subjects who did not receive rescue medication and had values measured at 26 weeks, the mean change from baseline for HbA1c was -1.1%, -1.1%, -1.1%, -1.5% and -1.6% for sitagliptin, ertugliflozin 5 mg, ertugliflozin 15 mg, ertugliflozin 5 mg + sitagliptin, and ertugliflozin 15 mg + sitagliptin, respectively.]
 | Sitagliptin 100 mg | Ertugliflozin 5 mg | Ertugliflozin 15 mg | Ertugliflozin 5 mg +Sitagliptin 100 mg | Ertugliflozin 15 mg + Sitagliptin 100 mg
HbA1c (%) | N = 242 | N = 244 | N = 247 | N = 237 | N = 241
Baseline (mean) | 8.5 | 8.6 | 8.6 | 8.6 | 8.6
Change from baseline (LS mean [Intent-to-treat analysis using ANCOVA adjusted for baseline value and baseline eGFR.]) | -1.0 | -1.0 | -1.0 | -1.4 | -1.4
Difference from
Sitagliptin |  |  |  | -0.4 [p<0.001 compared to control group.] (-0.6, -0.2) | -0.4 (-0.5, -0.2)
Ertugliflozin 5 mg |  |  |  | -0.4 (-0.5, -0.2)
Ertugliflozin 15 mg |  |  |  |  | -0.4 (-0.6, -0.2)
(LS mean, 95% CI)
Patients [N (%)] with HbA1c <7% | 93 (38.5) | 72 (29.3) | 83 (33.7) | 126 (53.3) | 123 (50.9)
FPG (mg/dL) | N = 246 | N = 250 | N = 247 | N = 240 | N = 241
Baseline (mean) | 177.4 | 184.1 | 179.5 | 183.8 | 177.2
Change from baseline (LS mean) | -24.3 | -34.0 | -34.6 | -41.1 | -44.3
Difference from
Sitagliptin |  |  |  | -16.8 (-23.2, -10.4) | -20.0 (-26.4, -13.6)
Ertugliflozin 5 mg |  |  |  | -7.0 [p<0.03 compared to control group.] (-13.3, -0.7)
Ertugliflozin 15 mg |  |  |  |  | -9.8 (-16.1, -3.4)
(LS mean, 95% CI)

The mean baseline body weight was 89.8 kg, 88.6 kg, 88.0 kg, 89.5 kg, and 87.5 kg in the sitagliptin 100 mg, ertugliflozin 5 mg, ertugliflozin 15 mg, ertugliflozin 5 mg + sitagliptin 100 mg, and ertugliflozin 15 mg + sitagliptin 100 mg groups, respectively. The mean changes from baseline to Week 26 were -0.4 kg, -2.6 kg, -3.4 kg, -2.4 kg, and -2.7 kg in the sitagliptin 100 mg, ertugliflozin 5 mg, ertugliflozin 15 mg, ertugliflozin 5 mg + sitagliptin 100 mg, and ertugliflozin 15 mg + sitagliptin 100 mg groups, respectively. The difference from sitagliptin 100 mg (95% CI) for ertugliflozin 5 mg + sitagliptin 100 mg was -1.9 kg (-2.6, -1.3) and for ertugliflozin 15 mg + sitagliptin 100 mg was -2.3 kg (-3.0, -1.6).

The mean baseline systolic blood pressure was 128.4 mmHg, 129.7 mmHg, 128.9 mmHg, 130.2 mmHg, and 129.1 mmHg in the sitagliptin 100 mg, ertugliflozin 5 mg, ertugliflozin 15 mg, ertugliflozin 5 mg + sitagliptin 100 mg, and ertugliflozin 15 mg + sitagliptin 100 mg groups, respectively. The mean changes from baseline to Week 26 were -0.5 mmHg, -4.0 mmHg, -3.6 mmHg, -2.8 mmHg, and -3.4 mmHg in the sitagliptin 100 mg, ertugliflozin 5 mg, ertugliflozin 15 mg, ertugliflozin 5 mg + sitagliptin 100 mg, and ertugliflozin 15 mg + sitagliptin 100 mg groups, respectively. The difference from sitagliptin 100 mg (95% CI) for ertugliflozin 5 mg + sitagliptin 100 mg was -2.3 mmHg (-4.3, -0.4) and for ertugliflozin 15 mg + sitagliptin 100 mg was -2.9 mmHg (-4.8, -1.0).

Figure 3: HbA1c (%) Change over Time in a Factorial Study with Ertugliflozin and Sitagliptin as Add-on Combination Therapy with Metformin HCl Compared to Individual Components Alone [Data to the left of the vertical line are observed means (non-model-based) excluding values occurring post glycemic rescue. Data to the right of the vertical line represent the final Week 26 data, including all values regardless of use of glycemic rescue medication and use of study drug, with missing Week 26 values imputed using multiple imputation (26-MI) with a mean equal to the baseline value of the patient (see Table 6).]

Ertugliflozin as Add-on Combination Therapy with Metformin HCl and Sitagliptin

A total of 463 patients with type 2 diabetes mellitus inadequately controlled (HbA1c between 7% and 10.5%) on metformin HCl (≥1,500 mg/day for ≥8 weeks) and sitagliptin 100 mg orally once daily participated in a randomized, double-blind, multi-center, 26-week, placebo-controlled study (NCT02036515) to evaluate the efficacy and safety of ertugliflozin. Patients entered a 2-week, single-blind, placebo run-in period and were randomized to placebo, ertugliflozin 5 mg, or ertugliflozin 15 mg.

At Week 26, treatment with ertugliflozin at 5 mg or 15 mg daily provided statistically significant reductions in in HbA1c. Ertugliflozin also resulted in a higher proportion of patients achieving an HbA1c <7% compared to placebo (see Table 7).

Table 7: Results at Week 26 from an Add-on Study of Ertugliflozin in Combination with Metformin HCl and Sitagliptin in Patients with Type 2 Diabetes Mellitus [N includes all randomized and treated patients with a baseline measurement of the outcome variable. At Week 26, the primary HbA1c endpoint was missing for 10%, 11%, and 7% of patients and during the trial, rescue medication was initiated by 16%, 1%, and 2% of patients randomized to placebo, ertugliflozin 5 mg, and ertugliflozin 15 mg, respectively. Missing Week 26 measurements were imputed using multiple imputation with a mean equal to the baseline value of the patient. Results included measurements collected after initiation of rescue medication. For those patients who did not receive rescue medication and had values measured at 26 weeks, the mean changes from baseline for HbA1c were -0.2%, -0.8%, and -0.9% for placebo, ertugliflozin 5 mg, and ertugliflozin 15 mg, respectively.]
 | Placebo | Ertugliflozin 5 mg | Ertugliflozin 15 mg
HbA1c (%) | N = 152 | N = 155 | N = 152
Baseline (mean) | 8.0 | 8.1 | 8.0
Change from baseline (LS mean [Intent-to-treat analysis using ANCOVA adjusted for baseline value, prior antihyperglycemic medication and baseline eGFR.]) | -0.2 | -0.7 | -0.8
Difference from placebo (LS mean, 95% CI) |  | -0.5 [p<0.001 compared to placebo.] (-0.7, -0.3) | -0.6 (-0.8, -0.4)
Patients [N (%)] with HbA1c <7% | 31 (20.2) | 54 (34.6) | 64 (42.3)
FPG (mg/dL) | N = 152 | N = 156 | N = 152
Baseline (mean) | 169.6 | 167.7 | 171.7
Change from baseline (LS mean) | -6.5 | -25.7 | -32.1
Difference from placebo (LS mean, 95% CI) |  | -19.2 (-26.8, -11.6) | -25.6 (-33.2, -18.0)

The mean baseline body weight was 86.5 kg, 87.6 kg, and 86.6 kg in the placebo, ertugliflozin 5 mg, and ertugliflozin 15 mg groups, respectively. The mean changes from baseline to Week 26 were -1.0 kg, -3.0 kg, and -2.8 kg in the placebo, ertugliflozin 5 mg and ertugliflozin 15 mg groups, respectively. The difference from placebo (95% CI) for ertugliflozin 5 mg was -1.9 kg (-2.6, -1.3) and for ertugliflozin 15 mg was -1.8 kg (-2.4, -1.2).

The mean baseline systolic blood pressure was 130.2 mmHg, 132.1 mmHg, and 131.6 mmHg in the placebo, ertugliflozin 5 mg, and ertugliflozin 15 mg groups, respectively. The mean changes from baseline to Week 26 were -0.2 mmHg, -3.8 mmHg, and -4.5 mmHg in the placebo, ertugliflozin 5 mg and ertugliflozin 15 mg groups, respectively. The difference from placebo (95% CI) for ertugliflozin 5 mg was -3.7 mmHg (-6.1, -1.2) and for ertugliflozin 15 mg was -4.3 mmHg (-6.7, -1.9).

Initial Combination Therapy of Ertugliflozin and Sitagliptin

A total of 291 patients with type 2 diabetes mellitus inadequately controlled (HbA1c between 8% and 10.5%) on diet and exercise participated in a randomized, double-blind, multi-center, placebo-controlled 26-week study (NCT02226003) to evaluate the efficacy and safety of ertugliflozin in combination with sitagliptin. These patients, who were not receiving any background antihyperglycemic treatment for ≥8 weeks, entered a 2-week, single-blind, placebo run-in period and were randomized to placebo, ertugliflozin 5 mg, or ertugliflozin 15 mg, in combination with sitagliptin (100 mg), orally once daily.

At Week 26, treatment with ertugliflozin 5 mg and 15 mg in combination with sitagliptin at 100 mg daily provided statistically significant reductions in HbA1c compared to placebo. Ertugliflozin 5 mg and 15 mg in combination with sitagliptin at 100 mg daily also resulted in a higher proportion of patients achieving an HbA1c <7% compared with placebo (see Table 8).

Table 8: Results at Week 26 from an Initial Combination Therapy Study of Ertugliflozin and Sitagliptin [N includes all randomized and treated patients with a baseline measurement of the outcome variable. At Week 26 the primary HbA1c endpoint was missing for 22%, 7% and 10% of patients and during the trial rescue medication was initiated by 32%, 6%, and 0% of patients randomized to placebo, ertugliflozin 5 mg and ertugliflozin 15 mg, respectively. Missing Week 26 measurements were imputed using multiple imputation with a mean equal to the baseline value of the patient. Results included measurements collected after initiation of rescue medication. For those subjects who did not receive rescue medication and had values measured at 26 weeks, the mean change from baseline for HbA1c was -0.8%, -1.7%, -1.7% for placebo, ertugliflozin 5 mg and ertugliflozin 15 mg, respectively.]
 | Placebo | Ertugliflozin 5 mg + Sitagliptin 100 mg | Ertugliflozin 15 mg + Sitagliptin 100 mg
HbA1c (%) | N = 96 | N = 98 | N = 96
Baseline (mean) | 9.0 | 8.9 | 9.0
Change from baseline (LS mean [Intent-to-treat analysis using ANCOVA adjusted for baseline value, prior antihyperglycemic medication and baseline eGFR.]) | -0.6 | -1.6 | -1.5
Difference from placebo (LS mean and 95% CI) |  | -1.0 [p<0.001 compared to placebo.] (-1.3, -0.7) | -0.9 (-1.3, -0.6)
Patients [N (%)] with HbA1c <7% | 9 (9.3) | 36 (37.1) | 32 (32.9)
FPG (mg/dL) | N = 96 | N = 98 | N = 96
Baseline (mean) | 207.5 | 198.0 | 187.7
Change from baseline (LS mean) | -11.8 | -47.1 | -50.8
Difference from placebo (LS mean, 95% CI) |  | -35.4 (-47.3, -23.4) | -39.1 (-51.4, -26.8)

The mean baseline body weight was 95.0 kg, 90.8 kg, and 91.2 kg in the placebo, ertugliflozin 5 mg + sitagliptin 100 mg, and ertugliflozin 15 mg + sitagliptin 100 mg groups, respectively. The mean changes from baseline to Week 26 were -0.5 kg, -2.7 kg, and -2.8 kg in the placebo, ertugliflozin 5 mg + sitagliptin 100 mg, and ertugliflozin 15 mg + sitagliptin 100 mg groups, respectively. The difference from placebo (95% CI) for ertugliflozin 5 mg + sitagliptin 100 mg was -2.1 kg (-3.1, -1.2) and for ertugliflozin 15 mg + sitagliptin 100 mg was -2.3 kg (-3.3, -1.3).

The mean baseline systolic blood pressure was 127.4 mmHg, 130.7 mmHg, and 129.2 mmHg in the placebo, ertugliflozin 5 mg + sitagliptin 100 mg, and ertugliflozin 15 mg + sitagliptin 100 mg groups, respectively. The mean changes from baseline to Week 26 were 1.6 mmHg, -2.4 mmHg, and -3.5 mmHg in the placebo, ertugliflozin 5 mg + sitagliptin 100 mg, and ertugliflozin 15 mg + sitagliptin 100 mg, respectively. The difference from placebo (95% CI) for ertugliflozin 5 mg + sitagliptin 100 mg was -4.0 mmHg (-7.2, -0.8) and for ertugliflozin 15 mg + sitagliptin 100 mg was -5.2 mmHg (-8.4, -1.9).

14.2 Ertugliflozin Cardiovascular Outcomes in Patients with Type 2 Diabetes Mellitus and Established Cardiovascular Disease

The effect of ertugliflozin on cardiovascular risk in adult patients with type 2 diabetes and established atherosclerotic cardiovascular disease was evaluated in the VERTIS CV study (NCT01986881), a multicenter, multi-national, randomized, double-blind, placebo-controlled, event driven trial. The study compared the risk of experiencing a major adverse cardiovascular event (MACE) between ertugliflozin and placebo when these were added to and used concomitantly with standard of care treatments for diabetes and atherosclerotic cardiovascular disease.

A total of 8,246 patients were randomized to placebo (N=2,747), oral once daily ertugliflozin 5 mg (N=2,752), or oral once daily ertugliflozin 15 mg (N=2,747) and followed for a median of 3 years. Approximately 88% of the study population was White, 6% Asian, and 3% Black or African American. The mean age was 64 years and approximately 70% were male.

All patients in the study had inadequately controlled type 2 diabetes mellitus at baseline (HbA1c greater than or equal to 7%). The mean duration of type 2 diabetes mellitus was 13 years, the mean HbA1c at baseline was 8.2% and the mean eGFR was 76 mL/min/1.73 m^2. At baseline, patients were treated with one (32%) or more (67%) antidiabetic medications including biguanides (metformin HCl) (76%), insulin (47%), sulfonylureas (41%), DPP-4 inhibitors (11%) and GLP-1 receptor agonists (3%).

Almost all patients (99%) had established atherosclerotic cardiovascular disease at baseline including: a documented history of coronary artery disease (76%), cerebrovascular disease (23%) or peripheral artery disease (19%). Approximately 24% patients had a history of heart failure (HF). At baseline, the mean systolic blood pressure was 133 mmHg, the mean diastolic blood pressure was 77 mmHg, the mean LDL was 89 mg/dL, and the mean HDL was 44 mg/dL. At baseline, approximately 81% of patients were treated with renin angiotensin system inhibitors, 69% with beta-blockers, 43% with diuretics, 82% with statins, 4% with ezetimibe, and 89% with antiplatelet agents.

The primary endpoint in VERTIS CV was the time to first occurrence of a Major Adverse Cardiac Event (MACE). A major adverse cardiovascular event was defined as occurrence of either a cardiovascular death or a nonfatal myocardial infarction (MI) or a nonfatal stroke. The statistical analysis plan pre-specified that the 5 and 15 mg doses would be combined for the analysis. A Cox proportional hazards model was used to test for non-inferiority against the pre-specified risk margin of 1.3 for the hazard ratio of MACE. Type I error was controlled across multiple tests using a hierarchical testing strategy.

The incidence rate of MACE was similar between the ertugliflozin-treated and placebo-treated patients. The estimated hazard ratio of MACE associated with ertugliflozin relative to placebo was 0.97 with 95.6% confidence interval (0.85, 1.11). The upper bound of this confidence interval excluded a risk larger than 1.3. (Table 9). Results for the 5 mg and 15 mg doses were consistent with results for the combined dose group.

Table 9: Analysis of MACE and its Components from the VERTIS-CV Study [Intent-to-treat analysis set.]
Endpoint [MACE was evaluated in subjects who took at least one dose of study medication and, for subjects who discontinued study medication prior to the end of the study, censored events that occurred more than 365 days after the last dose of study medication. Other endpoints were evaluated using all randomized subjects and events that occurred any time after the first dose of study medication until the last contact date. The total number of first events was analyzed for each endpoint.] | Placebo (N=2747) |  | Ertugliflozin (N=5499) |  | Hazard Ratio vs Placebo (CI) [HR and CI are based on Cox proportional hazards regression model, stratified by cohorts.]
Endpoint [MACE was evaluated in subjects who took at least one dose of study medication and, for subjects who discontinued study medication prior to the end of the study, censored events that occurred more than 365 days after the last dose of study medication. Other endpoints were evaluated using all randomized subjects and events that occurred any time after the first dose of study medication until the last contact date. The total number of first events was analyzed for each endpoint.] | N (%) | Event Rate (per 100 person-years) | N (%) | Event Rate (per 100 person-years) | Hazard Ratio vs Placebo (CI) [HR and CI are based on Cox proportional hazards regression model, stratified by cohorts.]
MACE (CV death, non-fatal MI, or non-fatal stroke) Composite | 327 (11.9) | 4.0 | 653 (11.9) | 3.9 | 0.97 (0.85, 1.11)
Components of Composite Endpoint
Non-fatal MI | 148 (5.4) | 1.6 | 310 (5.6) | 1.7 | 1.04 (0.86, 1.27)
Non-fatal Stroke | 78 (2.8) | 0.8 | 157 (2.9) | 0.8 | 1.00 (0.76, 1.32)
CV death | 184 (6.7) | 1.9 | 341 (6.2) | 1.8 | 0.92 (0.77, 1.11)
N=Number of patients, CI=Confidence interval, CV=Cardiovascular, MI=Myocardial infarction.

16 HOW SUPPLIED/STORAGE AND HANDLING

STEGLUJAN (ertugliflozin and sitagliptin) tablets are available in the strengths listed below:

Strength | Description | How Supplied | NDC
5 mg/100 mg tablets | beige, almond-shaped, debossed with “554” on one side and plain on the other side. | unit-of-use bottles of 30 | 0006-5367-03
5 mg/100 mg tablets | beige, almond-shaped, debossed with “554” on one side and plain on the other side. | unit-of-use bottles of 90 | 0006-5367-06
15 mg/100 mg tablets | brown, almond-shaped, debossed with “555” on one side and plain on the other side. | unit-of-use bottles of 30 | 0006-5368-03
15 mg/100 mg tablets | brown, almond-shaped, debossed with “555” on one side and plain on the other side. | unit-of-use bottles of 90 | 0006-5368-06

STORAGE AND HANDLING

Store at 20°C-25°C (68°F-77°F), excursions permitted between 15°C-30°C (between 59°F-86°F) [see USP Controlled Room Temperature]. Protect from moisture. Store in a dry place.

17 PATIENT COUNSELING INFORMATION

Advise the patient to read the FDA-approved patient labeling (Medication Guide).

Diabetic Ketoacidosis in Patients with Type 1 Diabetes Mellitus and Other Ketoacidosis

Inform patients that STEGLUJAN can cause potentially fatal ketoacidosis and that type 2 diabetes mellitus and pancreatic disorders (e.g., history of pancreatitis or pancreatic surgery) are risk factors.

Educate all patients on precipitating factors (such as insulin dose reduction or missed insulin doses, infection, reduced caloric intake, ketogenic diet, surgery, dehydration, and alcohol abuse) and symptoms of ketoacidosis (including nausea, vomiting, abdominal pain, tiredness, and labored breathing). Inform patients that blood glucose may be normal even in the presence of ketoacidosis.

Advise patients that they may be asked to monitor ketones. If symptoms of ketoacidosis occur, instruct patients to discontinue STEGLUJAN and seek medical attention immediately [see Warnings and Precautions (5.1)].

Pancreatitis

Inform patients that acute pancreatitis has been reported during use of sitagliptin, a component of STEGLUJAN. Inform patients that persistent severe abdominal pain, sometimes radiating to the back, which may or may not be accompanied by vomiting, is the hallmark symptom of acute pancreatitis. Instruct patients to promptly discontinue STEGLUJAN and contact their physician if persistent severe abdominal pain occurs [see Warnings and Precautions (5.2)].

Lower Limb Amputation

Inform patients of the potential for an increased risk of amputations. Counsel patients about the importance of routine preventative foot care. Instruct patients to monitor for new pain or tenderness, sores or ulcers, or infections involving the leg or foot and to seek medical advice immediately if such signs or symptoms develop [see Warnings and Precautions (5.3)].

Volume Depletion

Inform patients that symptomatic hypotension may occur with STEGLUJAN and advise them to contact their doctor if they experience such symptoms [see Warnings and Precautions (5.5)]. Inform patients that dehydration may increase the risk for hypotension, and to have adequate fluid intake.

Serious Urinary Tract Infections

Inform patients of the potential for urinary tract infections, which may be serious. Provide them with information on the symptoms of urinary tract infections. Advise them to seek medical advice if such symptoms occur [see Warnings and Precautions (5.6)].

Heart Failure

Inform patients of the signs and symptoms of heart failure. Instruct patients to contact their health care provider as soon as possible if they experience symptoms of heart failure, including increasing shortness of breath, rapid increase in weight or swelling of the feet [see Warnings and Precautions (5.7)].

Hypoglycemia with Concomitant Use of Insulin or Insulin Secretagogue

Inform patients that the incidence of hypoglycemia may increase when STEGLUJAN is used with insulin or an insulin secretagogue. Educate patients or caregivers on the signs and symptoms of hypoglycemia [see Warnings and Precautions (5.8)].

Necrotizing Fasciitis of the Perineum (Fournier’s Gangrene)

Inform patients that necrotizing infections of the perineum (Fournier’s Gangrene) have occurred with SGLT2 inhibitors. Counsel patients to promptly seek medical attention if they develop pain or tenderness, redness, or swelling of the genitals or the area from the genitals back to the rectum, along with a fever above 100.4°F or malaise [see Warnings and Precautions (5.9)].

Genital Mycotic Infections in Females (e.g., Vulvovaginitis)

Inform female patients that vaginal yeast infections may occur and provide them with information on the signs and symptoms of vaginal yeast infection. Advise them of treatment options and when to seek medical advice [see Warnings and Precautions (5.10)].

Genital Mycotic Infections in Males (e.g., Balanitis or Balanoposthitis)

Inform male patients that yeast infections of the penis (e.g., balanitis or balanoposthitis) may occur, especially in uncircumcised males. Provide them with information on the signs and symptoms of balanitis and balanoposthitis (rash or redness of the glans or foreskin of the penis). Advise them of treatment options and when to seek medical advice [see Warnings and Precautions (5.10)].

Hypersensitivity Reactions

Inform patients that allergic reactions have been reported during postmarketing use of sitagliptin, a component of STEGLUJAN. If symptoms of allergic reactions (including rash, hives, and swelling of the face, lips, tongue, and throat that may cause difficulty in breathing or swallowing) occur, instruct patients that they must stop taking STEGLUJAN and seek medical advice promptly [see Warnings and Precautions (5.11)].

Severe and Disabling Arthralgia

Inform patients that severe and disabling joint pain may occur with this class of drugs. The time to onset of symptoms can range from one day to years. Instruct patients to seek medical advice if severe joint pain occurs [see Warnings and Precautions (5.12)].

Bullous Pemphigoid

Inform patients that bullous pemphigoid may occur with the DPP-4 class of drugs. Instruct patients to seek medical advice if blisters or erosions occur [see Warnings and Precautions (5.13)].

Fetal Toxicity

Advise pregnant patients of the potential risk to a fetus with treatment with STEGLUJAN. Instruct patients to immediately inform their healthcare provider if pregnant or planning to become pregnant [see Use in Specific Populations (8.1)].

Lactation

Advise patients that use of STEGLUJAN is not recommended while breastfeeding [see Use in Specific Populations (8.2)].

Laboratory Tests

Due to the mechanism of action of ertugliflozin, inform patients that their urine will test positive for glucose while taking STEGLUJAN.

Missed Dose

Instruct patients to take STEGLUJAN only as prescribed. If a dose is missed, it should be taken as soon as the patient remembers. Advise patients not to double their next dose.

Manufactured for: Merck Sharp & Dohme LLC
Rahway, NJ 07065, USA

For patent information: www.msd.com/research/patent

Copyright © 2017-2024 Merck & Co., Inc., Rahway, NJ, USA, and its affiliates.
All rights reserved.

uspi-mk8835a-t-2412r015

Medication Guide
STEGLUJAN® [STEG-loo-jan]
(ertugliflozin and sitagliptin)
tablets, for oral use

Read this Medication Guide carefully before you start taking STEGLUJAN and each time you get a refill. There may be new information. This information does not take the place of talking with your healthcare provider about your medical condition or your treatment.

What is the most important information I should know about STEGLUJAN?

STEGLUJAN may cause serious side effects, including:

- Diabetic ketoacidosis (increased ketones in your blood or urine) in people with type 1 diabetes and other ketoacidosis. STEGLUJAN can cause ketoacidosis that can be life-threatening and may lead to death. Ketoacidosis is a serious condition which needs to be treated in a hospital. People with type 1 diabetes have a high risk of getting ketoacidosis. People with type 2 diabetes or pancreas problems also have an increased risk of getting ketoacidosis. Ketoacidosis can also happen in people who are sick, cannot eat or drink as usual, skip meals, are on a diet high in fat and low in carbohydrates (ketogenic diet), take less than the usual amount of insulin or miss insulin doses, drink too much alcohol, have a loss of too much fluid from the body (volume depletion), or who have surgery. Ketoacidosis can happen even if your blood sugar is less than 250 mg/dL. Your healthcare provider may ask you to periodically check ketones in your urine or blood.
  Stop taking STEGLUJAN and call your healthcare provider or get medical help right away if you get any of the following. If possible, check for ketones in your urine or blood, even if your blood sugar is less than 250 mg/dL:

- nausea
- vomiting
- stomach-area (abdominal) pain

- tiredness
- trouble breathing
- ketones in your urine or blood

- Inflammation of the pancreas (pancreatitis) which may be severe and lead to death. Certain medical problems make you more likely to get pancreatitis.
  Before you start taking STEGLUJAN, tell your healthcare provider if you have ever had:

- pancreatitis
- a history of alcoholism
- kidney problems

- stones in your gallbladder (gallstones)
- high blood triglyceride levels

Stop taking STEGLUJAN and call your healthcare provider right away if you have pain in your stomach area (abdomen) that is severe and will not go away. The pain may be felt going from your abdomen through to your back. The pain may happen with or without vomiting. These may be symptoms of pancreatitis.

- Amputations. STEGLUJAN may increase your risk of lower limb amputations.
  You may be at a higher risk of lower limb amputation if you:
  - have a history of amputation
  - have had blocked or narrowed blood vessels, usually in your leg
  - have damage to the nerves (neuropathy) in your leg
  - have had diabetic foot ulcers or sores

Call your healthcare provider right away if you have new pain or tenderness, any sores, ulcers, or infections in your leg or foot. Your healthcare provider may decide to stop your STEGLUJAN for a while if you have any of these signs or symptoms. Talk to your healthcare provider about proper foot care.

- Dehydration. STEGLUJAN can cause some people to become dehydrated (the loss of body water and salt). Dehydration may cause you to feel dizzy, faint, lightheaded, or weak, especially when you stand up (orthostatic hypotension). There have been reports of sudden worsening of kidney function in people who are taking STEGLUJAN.

You may be at risk of dehydration if you:

- take medicines to lower your blood pressure, including water pills (diuretics)
- are on a low sodium (salt) diet
- have kidney problems
- are 65 years of age or older

Talk to your healthcare provider about what you can do to prevent dehydration including how much fluid you should drink on a daily basis. Call your healthcare provider right away if you reduce the amount of food or liquid you drink, for example if you are sick or cannot eat, or you start to lose liquids from your body, for example from vomiting, diarrhea or being in the sun too long.

- Vaginal yeast infection. Symptoms of a vaginal yeast infection include:

- vaginal odor
- white or yellowish vaginal discharge (discharge may be lumpy or look like cottage cheese)
- vaginal itching

- Yeast infection of the penis (balanitis or balanoposthitis). Swelling of an uncircumcised penis may develop that makes it difficult to pull back the skin around the tip of the penis. Other symptoms of yeast infection of the penis include:

- redness, itching, or swelling of the penis
- foul smelling discharge from the penis

- rash of the penis
- pain in the skin around your penis

Talk to your healthcare provider about what to do if you get symptoms of a yeast infection of the vagina or penis. Your healthcare provider may suggest you use an over-the-counter antifungal medicine. Talk to your healthcare provider right away if you use an over-the-counter antifungal medicine and your symptoms do not go away.

- Heart failure. Heart failure means your heart does not pump blood well enough.
  Before you start taking STEGLUJAN, tell your healthcare provider if you have ever had heart failure or have problems with your kidneys. Contact your healthcare provider right away if you have any of the following symptoms:
  - increasing shortness of breath or trouble breathing, especially when you lie down
  - swelling or fluid retention, especially in the feet, ankles or legs
  - an unusually fast increase in weight
  - unusual tiredness

These may be symptoms of heart failure.

What is STEGLUJAN?

STEGLUJAN contains 2 prescription medicines called ertugliflozin (STEGLATRO®) and sitagliptin (JANUVIA®). STEGLUJAN is used in adults with type 2 diabetes to improve blood sugar (glucose) along with diet and exercise.

- STEGLUJAN is not recommended to decrease blood sugar (glucose) in people with type 1 diabetes.
- If you have had pancreatitis (inflammation of the pancreas) in the past, it is not known if you have a higher chance of getting pancreatitis while you take STEGLUJAN.
- It is not known if STEGLUJAN is safe and effective in children under 18 years of age.

Who should not take STEGLUJAN?

Do not take STEGLUJAN if you:

- have severe kidney problems, end stage renal disease (ESRD), or are on dialysis.
- are allergic to ertugliflozin, sitagliptin, or any of the ingredients in STEGLUJAN. See the end of this Medication Guide for a list of ingredients in STEGLUJAN. Symptoms of a serious allergic reaction to STEGLUJAN may include:
  - skin rash
  - raised red patches on your skin (hives)
  - swelling of the face, lips, tongue, and throat that may cause difficulty in breathing or swallowing

If you have any of these symptoms, stop taking STEGLUJAN and call your healthcare provider right away or go to the nearest hospital emergency room.

Before you take STEGLUJAN, tell your healthcare provider about all of your medical conditions, including if you:

- have type 1 diabetes or have had diabetic ketoacidosis.
- have a decrease in your insulin dose.
- have a serious infection.
- have a history of infection of the vagina or penis.
- have a history of amputation.
- have had blocked or narrowed blood vessels, usually in your leg.
- have damage to the nerves (neuropathy) in your leg.
- have had diabetic foot ulcers or sores.
- have kidney problems.
- have liver problems.
- have a history of urinary tract infections or problems with urination.
- are on a low sodium (salt) diet. Your healthcare provider may change your diet or your dose.
- are going to have surgery. Your healthcare provider may stop your STEGLUJAN before you have surgery. Talk to your healthcare provider if you are having surgery about when to stop taking STEGLUJAN and when to start it again.
- are eating less or there is a change in your diet.
- are dehydrated.
- have or have had problems with your pancreas, including pancreatitis or surgery on your pancreas.
- drink alcohol very often or drink a lot of alcohol in the short term (“binge” drinking).
- have ever had an allergic reaction to STEGLUJAN.
- are pregnant or plan to become pregnant. STEGLUJAN may harm your unborn baby. If you become pregnant while taking STEGLUJAN, your healthcare provider may switch you to a different medicine to control your blood sugar. Talk to your healthcare provider about the best way to control your blood sugar if you plan to become pregnant or while you are pregnant.
- are breastfeeding or plan to breastfeed. It is not known if STEGLUJAN passes into your breast milk. You should not breastfeed if you take STEGLUJAN.

Tell your healthcare provider about all of the medicines you take, including prescription and over-the-counter medicines, vitamins, and herbal supplements.

STEGLUJAN may affect the way other medicines work, and other medicines may affect how STEGLUJAN works.

Know the medicines you take. Keep a list of them to show your healthcare provider and pharmacist when you get a new medicine.

How should I take STEGLUJAN?

- Take STEGLUJAN by mouth 1 time in the morning each day, with or without food., exactly as your healthcare provider tells you to take it.
- Your healthcare provider may tell you to take STEGLUJAN along with other diabetes medicines. Low blood sugar can happen more often when STEGLUJAN is taken with certain other diabetes medicines. See "What are the possible side effects of STEGLUJAN?".
- If you miss a dose, take it as soon as you remember. If it is almost time for your next dose, skip the missed dose and take the medicine at the next regularly scheduled time. Do not take 2 doses of STEGLUJAN at the same time. Talk with your healthcare provider if you have questions about a missed dose.
- If you take too much STEGLUJAN, call your healthcare provider or go to the nearest hospital emergency room right away.
- When your body is under some types of stress, such as fever, trauma (such as a car accident), infection, or surgery, the amount of diabetes medicine you need may change. Tell your healthcare provider right away if you have any of these conditions and follow your healthcare provider’s instructions.
- STEGLUJAN will cause your urine to test positive for glucose.
- Your healthcare provider may do certain blood tests before you start STEGLUJAN and during treatment as needed. Your healthcare provider may change your dose of STEGLUJAN based on the results of your blood tests.

What are the possible side effects of STEGLUJAN?

STEGLUJAN may cause serious side effects, including:

See "What is the most important information I should know about STEGLUJAN?"

- Kidney problems (sometimes requiring dialysis). Sudden kidney injury has happened to people treated with STEGLUJAN. Talk to your healthcare provider right away if you:
  - reduce the amount of food or liquid you drink, for example, if you are sick or cannot eat or
  - you start to lose liquids from your body, for example, from vomiting, diarrhea or being in the sun too long

- Serious urinary tract infections. Serious urinary tract infections that may lead to hospitalization have happened in people who are taking STEGLUJAN. Tell your healthcare provider if you have any signs or symptoms of a urinary tract infection such as a burning feeling when passing urine, a need to urinate often, the need to urinate right away, pain in the lower part of your stomach (pelvis), or blood in the urine. Sometimes people may also have a fever, back pain, nausea, or vomiting.

- Low blood sugar (hypoglycemia). If you take STEGLUJAN with another medicine that can cause low blood sugar such as a sulfonylurea or insulin, your risk of getting low blood sugar is higher. The dose of your sulfonylurea or insulin may need to be lowered while you take STEGLUJAN. Signs and symptoms of low blood sugar may include:

- headache
- confusion
- hunger
- shaking or feeling jittery

- drowsiness
- dizziness
- fast heartbeat

- weakness
- sweating
- irritability

- A rare but serious bacterial infection that causes damage to the tissue under the skin (necrotizing fasciitis) in the area between and around the anus and genitals (perineum). Necrotizing fasciitis of the perineum has happened in women and men who take medicines that lower blood sugar in the same way as one of the medicines in STEGLUJAN. Necrotizing fasciitis of the perineum may lead to hospitalization, may require multiple surgeries, and may lead to death. Seek medical attention immediately if you have fever above 100.4°F or you are feeling very weak, tired or uncomfortable (malaise) and you develop any of the following symptoms in the area between and around your anus and genitals:

- pain or tenderness

- swelling

- redness of skin (erythema)

- Serious allergic reactions. If you have any symptoms of a serious allergic reaction, stop taking STEGLUJAN and call your healthcare provider right away or go to the nearest hospital emergency room. See “Who should not take STEGLUJAN?”. Your healthcare provider may give you a medicine for your allergic reaction and prescribe a different medicine for your diabetes.
- Joint pain. Some people who take medicines called DPP-4 inhibitors, one of the medicines in STEGLUJAN, may develop joint pain that can be severe. Call your healthcare provider if you have severe joint pain.
- Skin reaction. Some people who take medicines called DPP-4 inhibitors, one of the medicines in STEGLUJAN, may develop a skin reaction called bullous pemphigoid that can require treatment in a hospital. Tell your healthcare provider right away if you develop blisters or the breakdown of the outer layer of your skin (erosion). Your healthcare provider may tell you to stop taking STEGLUJAN.

The most common side effects of ertugliflozin include:

- vaginal yeast infections and yeast infections of the penis (See "What is the most important information I should know about STEGLUJAN?")
- changes in urination, including urgent need to urinate more often, in larger amounts, or at night.

The most common side effects of sitagliptin include:

- upper respiratory infection
- stuffy or runny nose and sore throat
- headache
- stomach upset and diarrhea

STEGLUJAN may have other side effects including swelling of the hands or legs. Swelling of the hands and legs can happen when sitagliptin, one of the medicines in STEGLUJAN, is used with rosiglitazone (Avandia®). Rosiglitazone is another type of diabetes medicine.

These are not all the possible side effects of STEGLUJAN.

Call your healthcare provider for medical advice about side effects. You may report side effects to FDA at 1-800-FDA-1088.

How should I store STEGLUJAN?

- Store STEGLUJAN at room temperature between 68°F to 77°F (20°C to 25°C).
- Keep STEGLUJAN dry.

Keep STEGLUJAN and all medicines out of the reach of children.

General information about the safe and effective use of STEGLUJAN.

Medicines are sometimes prescribed for purposes other than those listed in a Medication Guide. Do not use STEGLUJAN for a condition for which it was not prescribed. Do not give STEGLUJAN to other people, even if they have the same symptoms that you have. It may harm them. You can ask your pharmacist or healthcare provider for information about STEGLUJAN that is written for health professionals.

For more information about STEGLUJAN, go to www.steglujan.com or call 1-800-622-4477.

What are the ingredients in STEGLUJAN?

Active ingredients: ertugliflozin and sitagliptin.

Inactive ingredients: microcrystalline cellulose, dibasic calcium phosphate anhydrous, croscarmellose sodium, sodium stearyl fumarate, magnesium stearate, and propyl gallate.

The tablet film coating contains the following inactive ingredients: hypromellose, hydroxypropyl cellulose, titanium dioxide, iron oxide red, iron oxide yellow, ferrosoferric oxide/black iron oxide, and carnauba wax.

Manufactured for: Merck Sharp & Dohme LLC
Rahway, NJ 07065, USA

For patent information, go to: www.msd.com/research/patent
Copyright © 2017-2023 Merck & Co., Inc., Rahway, NJ, USA, and its affiliates. All rights reserved.

usmg-mk8835a-t-2310r010

This Medication Guide has been approved by the U.S. Food and Drug Administration.

Revised: 10/2023

PRINCIPAL DISPLAY PANEL - 5 mg/100 mg Tablet Bottle Label

NDC 0006-5367-03

Steglujan®
(ertugliflozin and
sitagliptin) tablets

5 mg / 100 mg

Dispense the accompanying Medication Guide
to each patient.

Each tablet contains 6.48 mg ertugliflozin L-pyroglutamic
acid (equivalent to 5 mg ertugliflozin) and 128.5 mg
of sitagliptin phosphate (equivalent to 100 mg sitagliptin).

Rx only

30 Tablets

PRINCIPAL DISPLAY PANEL - 15 mg/100 mg Tablet Bottle Label

NDC 0006-5368-03

Steglujan®
(ertugliflozin and
sitagliptin) tablets

15 mg / 100 mg

Dispense the accompanying Medication Guide
to each patient.

Each tablet contains 19.43 mg ertugliflozin L-pyroglutamic
acid (equivalent to 15 mg ertugliflozin) and 128.5 mg
of sitagliptin phosphate (equivalent to 100 mg sitagliptin).

Rx only

30 Tablets